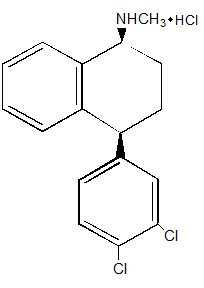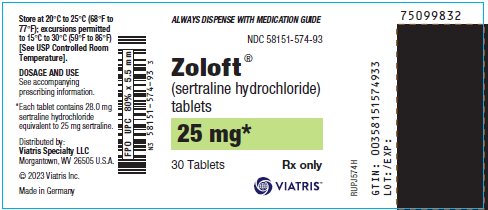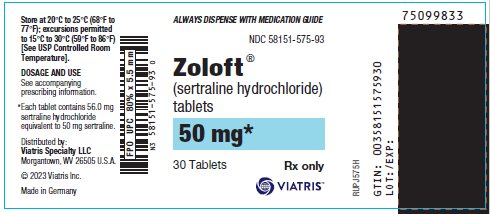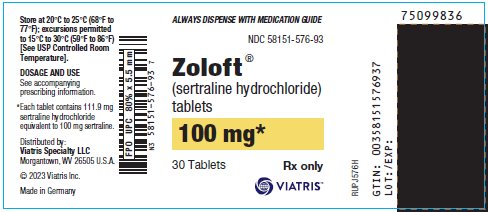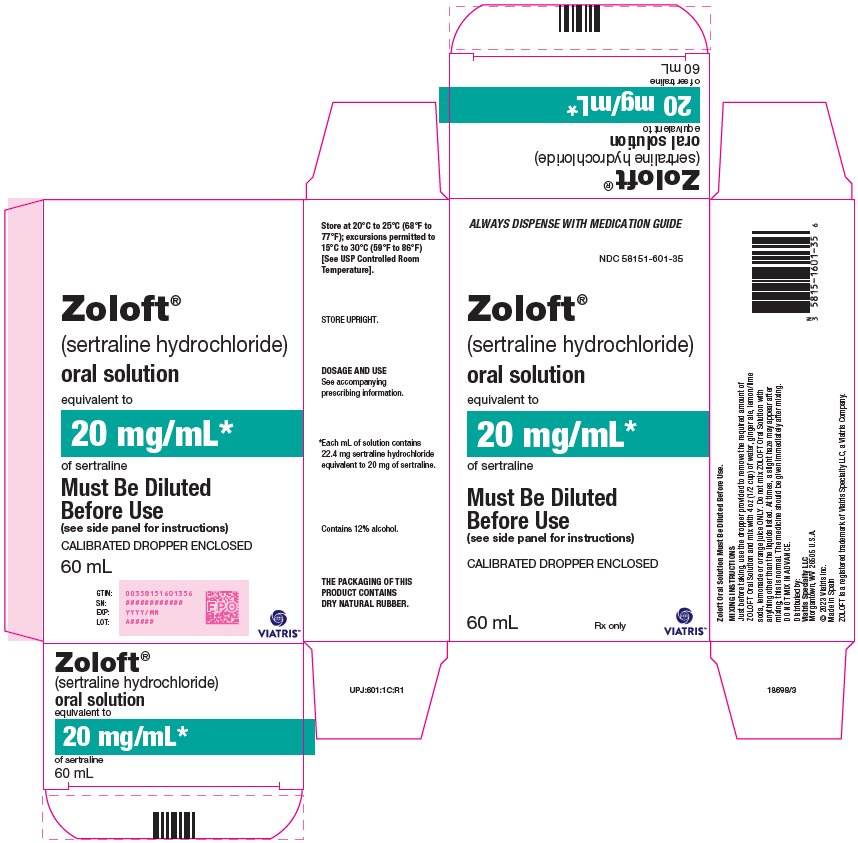 DRUG LABEL: Zoloft
NDC: 58151-574 | Form: TABLET, FILM COATED
Manufacturer: Viatris Specialty LLC
Category: prescription | Type: HUMAN PRESCRIPTION DRUG LABEL
Date: 20230808

ACTIVE INGREDIENTS: SERTRALINE HYDROCHLORIDE 25 mg/1 1
INACTIVE INGREDIENTS: DIBASIC CALCIUM PHOSPHATE DIHYDRATE; D&C YELLOW NO. 10; FD&C BLUE NO. 1; FD&C RED NO. 40; HYDROXYPROPYL CELLULOSE (1600000 WAMW); HYPROMELLOSE, UNSPECIFIED; MAGNESIUM STEARATE; MICROCRYSTALLINE CELLULOSE; POLYETHYLENE GLYCOL, UNSPECIFIED; POLYSORBATE 80; TITANIUM DIOXIDE; ALUMINUM OXIDE; SODIUM STARCH GLYCOLATE TYPE A POTATO

HIGHLIGHTS OF PRESCRIBING INFORMATION

These highlights do not include all the information needed to use ZOLOFT safely and effectively. See full prescribing information for ZOLOFT.
ZOLOFT (sertraline hydrochloride) tablets, for oral use
ZOLOFT (sertraline hydrochloride) oral solution
Initial U.S. Approval: 1991

RECENT MAJOR CHANGES

Warnings and Precautions (5.2, 5.3) 8/2023

WARNING: SUICIDAL THOUGHTS AND BEHAVIORS

See full prescribing information for complete boxed warning.

- Antidepressants increased the risk of suicidal thoughts and behaviors in pediatric and young adult patients (5.1)
- Closely monitor for clinical worsening and emergence of suicidal thoughts and behaviors (5.1)

1 INDICATIONS AND USAGE

ZOLOFT is a selective serotonin reuptake inhibitor (SSRI) indicated for the treatment of (1):

- Major depressive disorder (MDD)
- Obsessive-compulsive disorder (OCD)
- Panic disorder (PD)
- Posttraumatic stress disorder (PTSD)
- Social anxiety disorder (SAD)
- Premenstrual dysphoric disorder (PMDD)

2 DOSAGE AND ADMINISTRATION

Indication | Starting Dosage | Maximum Dosage
MDD (2.1) | 50 mg per day | 200 mg per day
OCD (2.1) | 25 mg per day (ages 6-12); 50 mg per day (ages ≥ 13) | 200 mg per day
PD, PTSD, SAD (2.1) | 25 mg per day | 200 mg per day
PMDD (2.2) continuous dosing | 50 mg per day | 150 mg per day
PMDD (2.2) intermittent dosing | 50 mg per day during luteal phase only | 100 mg per day during luteal phase only

- If inadequate response to starting dosage, titrate in 25-50 mg per day increments once weekly in MDD, OCD, PD, PTSD, and SAD (2.1)
- See Full Prescribing Information for titration in PMDD (2.2)
- Hepatic impairment:
- Mild: Recommended starting and maximum dosage is half recommended dosage (2.4)
- Moderate or severe: Not recommended (2.4)
- When discontinuing ZOLOFT, reduce dose gradually (2.6, 5.4)
- Oral solution: Must be diluted before administration (2.7)

3 DOSAGE FORMS AND STRENGTHS

- Tablets: 25 mg, 50 mg and 100 mg (3)
- Oral solution: 20 mg/mL (3)

4 CONTRAINDICATIONS

- Concomitant use of monoamine oxidase inhibitors (MAOIs), or use within 14 days of stopping MAOIs (4, 7.1)
- Concomitant use of pimozide (4, 7.1)
- Known hypersensitivity to sertraline or excipients (4, 5.4)
- ZOLOFT oral solution only: Concomitant use of disulfiram (4)

5 WARNINGS AND PRECAUTIONS

- Serotonin Syndrome: Increased risk when co-administered with other serotonergic agents, but also when taken alone. If it occurs, discontinue ZOLOFT and serotonergic agents and initiate supportive treatment. (5.2)
- Increased Risk of Bleeding: Concomitant use of aspirin, nonsteroidal anti-inflammatory drugs (NSAIDs), other antiplatelet drugs, warfarin, and other anticoagulants may increase this risk. (5.3)
- Activation of Mania/Hypomania: Screen patients for bipolar disorder. (5.4)
- Seizures: Use with caution in patients with seizure disorders. (5.6)
- Angle Closure Glaucoma: Avoid use of antidepressants, including ZOLOFT, in patients with untreated anatomically narrow angles. (5.7)
- QTc Prolongation: ZOLOFT should be used with caution in patients with risk factors for QTc prolongation. (5.10)
- Sexual Dysfunction: ZOLOFT may cause symptoms of sexual dysfunction. (5.11)

6 ADVERSE REACTIONS

Most common adverse reactions (≥5% and twice placebo) in pooled placebo-controlled MDD, OCD, PD, PTSD, SAD and PMDD clinical trials were nausea, diarrhea/loose stool, tremor, dyspepsia, decreased appetite, hyperhidrosis, ejaculation failure, and decreased libido. (6.1)

To report SUSPECTED ADVERSE REACTIONS, contact Viatris at 1-877-446-3679 (1-877-4-INFO-RX) or FDA at 1-800-FDA-1088 or www.fda.gov/medwatch.

7 DRUG INTERACTIONS

- Protein-bound drugs: Monitor for adverse reactions and reduce dosage of ZOLOFT or other protein-bound drugs (e.g., warfarin) as warranted. (7.1, 12.3)
- CYP2D6 substrates: Reduce dosage of drugs metabolized by CYP2D6. (7.1, 12.3)

8 USE IN SPECIFIC POPULATIONS

- Pregnancy: Third trimester use may increase risk for persistent pulmonary hypertension and withdrawal in the neonate. (8.1)
- Pediatric use: Safety and effectiveness of ZOLOFT in pediatric patients other than those with OCD have not been established. (8.4)

FULL PRESCRIBING INFORMATION

WARNING: SUICIDAL THOUGHTS AND BEHAVIORS

Antidepressants increased the risk of suicidal thoughts and behavior in pediatric and young adult patients in short-term studies. Closely monitor all antidepressant-treated patients for clinical worsening, and for emergence of suicidal thoughts and behaviors [See Warnings and Precautions (5.1)].

1 INDICATIONS AND USAGE

ZOLOFT is indicated for the treatment of the following [See Clinical Studies (14)]:

- Major depressive disorder (MDD)
- Obsessive-compulsive disorder (OCD)
- Panic disorder (PD)
- Posttraumatic stress disorder (PTSD)
- Social anxiety disorder (SAD)
- Premenstrual dysphoric disorder (PMDD)

2 DOSAGE AND ADMINISTRATION

2.1 Dosage in Patients with MDD, OCD, PD, PTSD, and SAD

The recommended initial dosage and maximum ZOLOFT dosage in patients with MDD, OCD, PD, PTSD, and SAD are displayed in Table 1 below. A dosage of 25 mg or 50 mg per day is the initial therapeutic dosage.

For adults and pediatric patients, subsequent dosages may be increased in case of an inadequate response in 25 to 50 mg per day increments once a week, depending on tolerability, up to a maximum of 200 mg per day. Given the 24-hour elimination half-life of ZOLOFT, the recommended interval between dose changes is one week.

Table 1: Recommended Daily Dosage of ZOLOFT in Patients with MDD, OCD, PD, PTSD, and SAD
Indication | Starting Dose | Therapeutic Range
Adults
MDD | 50 mg | 50-200 mg
OCD | 50 mg | 50-200 mg
PD, PTSD, SAD | 25 mg | 50-200 mg
Pediatric Patients
OCD (ages 6-12 years old) | 25 mg | 50-200 mg
OCD (ages 13-17 years old) | 50 mg | 50-200 mg

2.2 Dosage in Patients with PMDD

The recommended starting ZOLOFT dosage in adult women with PMDD is 50 mg per day. ZOLOFT may be administered either continuously (every day throughout the menstrual cycle) or intermittently (only during the luteal phase of the menstrual cycle, i.e., starting the daily dosage 14 days prior to the anticipated onset of menstruation and continuing through the onset of menses). Intermittent dosing would be repeated with each new cycle.

- When dosing continuously, patients not responding to a 50 mg dosage may benefit from dosage increases at 50 mg increments per menstrual cycle up to 150 mg per day.
- When dosing intermittently, patients not responding to a 50 mg dosage may benefit from increasing the dosage up to a maximum of 100 mg per day during the next menstrual cycle (and subsequent cycles) as follows: 50 mg per day during the first 3 days of dosing followed by 100 mg per day during the remaining days in the dosing cycle.

2.3 Screen for Bipolar Disorder Prior to Starting ZOLOFT

Prior to initiating treatment with ZOLOFT or another antidepressant, screen patients for a personal or family history of bipolar disorder, mania, or hypomania [See Warnings and Precautions (5.4)].

2.4 Dosage Modifications in Patients with Hepatic Impairment

Both the recommended starting dosage and therapeutic range in patients with mild hepatic impairment (Child Pugh scores 5 or 6) are half the recommended daily dosage [See Dosage and Administration (2.1, 2.2)]. The use of ZOLOFT in patients with moderate (Child Pugh scores 7 to 9) or severe hepatic impairment (Child Pugh scores 10-15) is not recommended [See Use in Specific Populations (8.6), Clinical Pharmacology (12.3)].

2.5 Switching Patients to or from a Monoamine Oxidase Inhibitor Antidepressant

At least 14 days must elapse between discontinuation of a monoamine oxidase inhibitor (MAOI) antidepressant and initiation of ZOLOFT. In addition, at least 14 days must elapse after stopping ZOLOFT before starting an MAOI antidepressant [See Contraindications (4), Warnings and Precautions (5.2)].

2.6 Discontinuation of Treatment with ZOLOFT

Adverse reactions may occur upon discontinuation of ZOLOFT [See Warnings and Precautions (5.5)]. Gradually reduce the dosage rather than stopping ZOLOFT abruptly whenever possible.

2.7 Preparation of ZOLOFT Oral Solution

ZOLOFT oral solution must be diluted before use.

- Use the supplied calibrated dropper to measure the amount of ZOLOFT oral solution needed
- Note: The supplied calibrated dropper has 25 mg and 50 mg graduation marks only
- Mix with 4 ounces (1/2 cup) of water, ginger ale, lemon/lime soda, lemonade or orange juice ONLY. After mixing, a slight haze may appear, which is normal.

Instruct patients or caregivers to immediately take the dose after mixing.

3 DOSAGE FORMS AND STRENGTHS

25 mg tablets: light green film-coated, engraved on one side with “ZOLOFT” and on the other side scored and engraved with “25 mg”

50 mg tablets: light blue film-coated, engraved on one side with “ZOLOFT” and on the other side scored and engraved with “50 mg”

100 mg tablets: light yellow film-coated, engraved on one side with “ZOLOFT” and on the other side scored and engraved with “100 mg”

Oral solution: a clear, colorless solution with a menthol scent containing sertraline hydrochloride equivalent to 20 mg of sertraline per mL and 12% alcohol. It is supplied as a 60 mL bottle with an accompanying calibrated dropper that has 25 mg and 50 mg graduation marks.

4 CONTRAINDICATIONS

ZOLOFT is contraindicated in patients:

- Taking, or within 14 days of stopping, MAOIs, (including the MAOIs linezolid and intravenous methylene blue) because of an increased risk of serotonin syndrome [See Warnings and Precautions (5.2), Drug Interactions (7.1)].
- Taking pimozide [See Drug Interactions (7.1)].
- With known hypersensitivity to sertraline (e.g., anaphylaxis, angioedema) [See Adverse Reactions (6.1, 6.2)].

In addition to the contraindications for all ZOLOFT formulations listed above, ZOLOFT oral solution is contraindicated in patients:

- Taking disulfiram. ZOLOFT oral solution contains alcohol, and concomitant use of ZOLOFT and disulfiram may result in a disulfiram-alcohol reaction.

5 WARNINGS AND PRECAUTIONS

5.1 Suicidal Thoughts and Behaviors in Pediatric and Young Adult Patients

In pooled analyses of placebo-controlled trials of antidepressant drugs (SSRIs and other antidepressant classes) that included approximately 77,000 adult patients and over 4,400 pediatric patients, the incidence of suicidal thoughts and behaviors in pediatric and young adult patients was greater in antidepressant-treated patients than in placebo-treated patients. The drug-placebo differences in the number of cases of suicidal thoughts and behaviors per 1000 patients treated are provided in Table 2.

No suicides occurred in any of the pediatric studies. There were suicides in the adult studies, but the number was not sufficient to reach any conclusion about antidepressant drug effect on suicide.

Table 2: Risk Differences of the Number of Cases of Suicidal Thoughts or Behaviors in the Pooled Placebo-Controlled Trials of Antidepressants in Pediatric and Adult Patients
Age Range (years) | Drug-Placebo Difference in Number of Patients of Suicidal Thoughts or Behaviors per 1000 Patients Treated
 | Increases Compared to Placebo
<18 | 14 additional patients
18-24 | 5 additional patients
 | Decreases Compared to Placebo
25-64 | 1 fewer patient
≥65 | 6 fewer patients

It is unknown whether the risk of suicidal thoughts and behaviors in pediatric and young adult patients extends to longer-term use, i.e., beyond four months. However, there is substantial evidence from placebo-controlled maintenance trials in adults with MDD that antidepressants delay the recurrence of depression.

Monitor all antidepressant-treated patients for clinical worsening and emergence of suicidal thoughts and behaviors, especially during the initial few months of drug therapy and at times of dosage changes. Counsel family members or caregivers of patients to monitor for changes in behavior and to alert the healthcare provider. Consider changing the therapeutic regimen, including possibly discontinuing ZOLOFT, in patients whose depression is persistently worse, or who are experiencing emergent suicidal thoughts or behaviors.

5.2 Serotonin Syndrome

Serotonin-norepinephrine reuptake inhibitors (SNRIs) and selective serotonin reuptake inhibitors (SSRIs), including ZOLOFT, can precipitate serotonin syndrome, a potentially life-threatening condition. The risk is increased with concomitant use of other serotonergic drugs (including triptans, tricyclic antidepressants, fentanyl, lithium, tramadol, meperidine, methadone, tryptophan, buspirone, amphetamines, and St. John’s Wort) and with drugs that impair metabolism of serotonin, i.e., MAOIs [See Contraindications (4), Drug Interactions (7.1)]. Serotonin syndrome can also occur when these drugs are used alone.

Serotonin syndrome signs and symptoms may include mental status changes (e.g., agitation, hallucinations, delirium, and coma), autonomic instability (e.g., tachycardia, labile blood pressure, dizziness, diaphoresis, flushing, hyperthermia), neuromuscular symptoms (e.g., tremor, rigidity, myoclonus, hyperreflexia, incoordination), seizures, and gastrointestinal symptoms (e.g., nausea, vomiting, diarrhea).

The concomitant use of ZOLOFT with MAOIs is contraindicated. In addition, do not initiate ZOLOFT in a patient being treated with MAOIs such as linezolid or intravenous methylene blue. No reports involved the administration of methylene blue by other routes (such as oral tablets or local tissue injection). If it is necessary to initiate treatment with an MAOI such as linezolid or intravenous methylene blue in a patient taking ZOLOFT, discontinue ZOLOFT before initiating treatment with the MAOI [See Contraindications (4), Drug Interactions (7.1)].

Monitor all patients taking ZOLOFT for the emergence of serotonin syndrome. Discontinue treatment with ZOLOFT and any concomitant serotonergic agents immediately if the above symptoms occur, and initiate supportive symptomatic treatment. If concomitant use of ZOLOFT with other serotonergic drugs is clinically warranted, inform patients of the increased risk for serotonin syndrome and monitor for symptoms.

5.3 Increased Risk of Bleeding

Drugs that interfere with serotonin reuptake inhibition, including ZOLOFT, increase the risk of bleeding events. Concomitant use of aspirin, nonsteroidal anti-inflammatory drugs (NSAIDs), other antiplatelet drugs, warfarin, and other anticoagulants may add to this risk. Case reports and epidemiological studies (case-control and cohort design) have demonstrated an association between use of drugs that interfere with serotonin reuptake and the occurrence of gastrointestinal bleeding. Based on data from the published observational studies, exposure to SSRIs, particularly in the month before delivery, has been associated with a less than 2-fold increase in the risk of postpartum hemorrhage [see Use in Specific Populations (8.1)]. Bleeding events related to drugs that interfere with serotonin reuptake have ranged from ecchymosis, hematoma, epistaxis, and petechiae to life-threatening hemorrhages.

Inform patients of the increased risk of bleeding associated with the concomitant use of ZOLOFT and antiplatelet agents or anticoagulants. For patients taking warfarin, carefully monitor the international normalized ratio.

5.4 Activation of Mania or Hypomania

In patients with bipolar disorder, treating a depressive episode with ZOLOFT or another antidepressant may precipitate a mixed/manic episode. In controlled clinical trials, patients with bipolar disorder were generally excluded; however, symptoms of mania or hypomania were reported in 0.4% of patients treated with ZOLOFT. Prior to initiating treatment with ZOLOFT, screen patients for any personal or family history of bipolar disorder, mania, or hypomania.

5.5 Discontinuation Syndrome

Adverse reactions after discontinuation of serotonergic antidepressants, particularly after abrupt discontinuation, include: nausea, sweating, dysphoric mood, irritability, agitation, dizziness, sensory disturbances (e.g., paresthesia, such as electric shock sensations), tremor, anxiety, confusion, headache, lethargy, emotional lability, insomnia, hypomania, tinnitus, and seizures. A gradual reduction in dosage rather than abrupt cessation is recommended whenever possible [See Dosage and Administration (2.6)].

5.6 Seizures

ZOLOFT has not been systematically evaluated in patients with seizure disorders. Patients with a history of seizures were excluded from clinical studies. ZOLOFT should be prescribed with caution in patients with a seizure disorder.

5.7 Angle-Closure Glaucoma

The pupillary dilation that occurs following use of many antidepressant drugs including ZOLOFT may trigger an angle closure attack in a patient with anatomically narrow angles who does not have a patent iridectomy. Avoid use of antidepressants, including ZOLOFT, in patients with untreated anatomically narrow angles.

5.8 Hyponatremia

Hyponatremia may occur as a result of treatment with SNRIs and SSRIs, including ZOLOFT. Cases with serum sodium lower than 110 mmol/L have been reported. Signs and symptoms of hyponatremia include headache, difficulty concentrating, memory impairment, confusion, weakness, and unsteadiness, which may lead to falls. Signs and symptoms associated with more severe or acute cases have included hallucination, syncope, seizure, coma, respiratory arrest, and death. In many cases, this hyponatremia appears to be the result of the syndrome of inappropriate antidiuretic hormone secretion (SIADH).

In patients with symptomatic hyponatremia, discontinue ZOLOFT and institute appropriate medical intervention. Elderly patients, patients taking diuretics, and those who are volume-depleted may be at greater risk of developing hyponatremia with SSRIs and SNRIs [See Use in Specific Populations (8.5)].

5.9 False-Positive Effects on Screening Tests for Benzodiazepines

False-positive urine immunoassay screening tests for benzodiazepines have been reported in patients taking ZOLOFT. This finding is due to lack of specificity of the screening tests. False-positive test results may be expected for several days following discontinuation of ZOLOFT. Confirmatory tests, such as gas chromatography/mass spectrometry, will help distinguish ZOLOFT from benzodiazepines [See Drug Interactions (7.3)].

5.10 QTc Prolongation

During post-marketing use of sertraline, cases of QTc prolongation and Torsade de Pointes (TdP) have been reported. Most reports were confounded by other risk factors. In a randomized, double-blind, placebo- and positive-controlled three-period crossover thorough QTc study in 54 healthy adult subjects, there was a positive relationship between the length of the rate-adjusted QTc interval and serum sertraline concentration. Therefore, ZOLOFT should be used with caution in patients with risk factors for QTc prolongation [See Drug Interactions (7.1), Clinical Pharmacology (12.2)].

5.11 Sexual Dysfunction

Use of SSRIs, including ZOLOFT, may cause symptoms of sexual dysfunction [see Adverse Reactions (6.1)]. In male patients, SSRI use may result in ejaculatory delay or failure, decreased libido, and erectile dysfunction. In female patients, SSRI use may result in decreased libido and delayed or absent orgasm.

It is important for prescribers to inquire about sexual function prior to initiation of ZOLOFT and to inquire specifically about changes in sexual function during treatment, because sexual function may not be spontaneously reported. When evaluating changes in sexual function, obtaining a detailed history (including timing of symptom onset) is important because sexual symptoms may have other causes, including the underlying psychiatric disorder. Discuss potential management strategies to support patients in making informed decisions about treatment.

6 ADVERSE REACTIONS

The following adverse reactions are described in more detail in other sections of the prescribing information:

- Hypersensitivity reactions to sertraline [See Contraindications (4)]
- Disulfiram-alcohol reaction when ZOLOFT oral solution is taken with disulfiram [See Contraindications (4)]
- QTc prolongation and ventricular arrhythmias when taken with pimozide [See Contraindications (4), Clinical Pharmacology (12.2)]
- Suicidal thoughts and behaviors [See Warnings and Precautions (5.1)]
- Serotonin syndrome [See Contraindications (4), Warnings and Precautions (5.2), Drug Interactions (7.1)]
- Increased risk of bleeding [See Warnings and Precautions (5.3)]
- Activation of mania/hypomania [See Warnings and Precautions (5.4)]
- Discontinuation syndrome [See Warnings and Precautions (5.5)]
- Seizures [See Warnings and Precautions (5.6)]
- Angle-closure glaucoma [See Warnings and Precautions (5.7)]
- Hyponatremia [See Warnings and Precautions (5.8)]
- Sexual Dysfunction [See Warnings and Precautions (5.11)]

6.1 Clinical Trials Experience

Because clinical trials are conducted under widely varying conditions, adverse reaction rates observed in the clinical trials of a drug cannot be directly compared to rates in the clinical trials of another drug and may not reflect the rates observed in practice.

The data described below are from randomized, double-blind, placebo-controlled trials of ZOLOFT (mostly 50 mg to 200 mg per day) in 3066 adults diagnosed with MDD, OCD, PD, PTSD, SAD, and PMDD. These 3066 patients exposed to ZOLOFT for 8 to12 weeks represent 568 patient-years of exposure. The mean age was 40 years; 57% were females and 43% were males.

The most common adverse reactions (≥5% and twice placebo) in all pooled placebo-controlled clinical trials of all ZOLOFT-treated patients with MDD, OCD, PD, PTSD, SAD and PMDD were nausea, diarrhea/loose stool, tremor, dyspepsia, decreased appetite, hyperhidrosis, ejaculation failure, and decreased libido (see Table 3). The following are the most common adverse reactions in trials of ZOLOFT (≥5% and twice placebo) by indication that were not mentioned previously.

- MDD: somnolence;
- OCD: insomnia, agitation;
- PD: constipation, agitation;
- PTSD: fatigue;
- PMDD: somnolence, dry mouth, dizziness, fatigue, and abdominal pain;
- SAD: insomnia, dizziness, fatigue, dry mouth, malaise.

Table 3: Common Adverse Reactions in Pooled Placebo-Controlled Trials in Adults with MDD, OCD, PD, PTSD, SAD, and PMDD [Adverse reactions that occurred greater than 2% in ZOLOFT-treated patients and at least 2% greater in ZOLOFT-treated patients than placebo-treated patients.]
 | ZOLOFT (N=3066) | Placebo (N=2293)
Cardiac disorders
Palpitations | 4% | 2%
Eye disorders
Visual impairment | 4% | 2%
Gastrointestinal disorders
Nausea | 26% | 12%
Diarrhea/Loose stools | 20% | 10%
Dry mouth | 14% | 9%
Dyspepsia | 8% | 4%
Constipation | 6% | 4%
Vomiting | 4% | 1%
General disorders and administration site conditions
Fatigue | 12% | 8%
Metabolism and nutrition disorders
Decreased appetite | 7% | 2%
Nervous system disorders
Dizziness | 12% | 8%
Somnolence | 11% | 6%
Tremor | 9% | 2%
Psychiatric disorders
Insomnia | 20% | 13%
Agitation | 8% | 5%
Libido decreased | 6% | 2%
Reproductive system and breast disorders
Ejaculation failure [Denominator used was for male patients only (n=1316 ZOLOFT; n=973 placebo).] | 8% | 1%
Erectile dysfunction | 4% | 1%
Ejaculation disorder | 3% | 0%
Male sexual dysfunctiom | 2% | 0%
Skin and subcutaneous tissue disorders
Hyperhidrosis | 7% | 3%

Adverse Reactions Leading to Discontinuation in Placebo-Controlled Clinical Trials

In all placebo-controlled studies in patients with MDD, OCD, PD, PTSD, SAD and PMDD, 368 (12%) of the 3066 patients who received ZOLOFT discontinued treatment due to an adverse reaction, compared with 93 (4%) of the 2293 placebo-treated patients. In placebo-controlled studies, the following were the common adverse reactions leading to discontinuation in ZOLOFT-treated patients:

- MDD, OCD, PD, PTSD, SAD and PMDD: nausea (3%), diarrhea (2%), agitation (2%), and insomnia (2%).
- MDD (>2% and twice placebo): decreased appetite, dizziness, fatigue, headache, somnolence, tremor, and vomiting.
- OCD: somnolence.
- PD: nervousness and somnolence.

Male and Female Sexual Dysfunction

Although changes in sexual desire, sexual performance and sexual satisfaction often occur as manifestations of a psychiatric disorder, they may also be a consequence of SSRI treatment. However, reliable estimates of the incidence and severity of untoward experiences involving sexual desire, performance and satisfaction are difficult to obtain, in part because patients and healthcare providers may be reluctant to discuss them. Accordingly, estimates of the incidence of untoward sexual experience and performance cited in labeling may underestimate their actual incidence.

Table 4 below displays the incidence of sexual adverse reactions reported by at least 2% of ZOLOFT-treated patients and twice placebo from pooled placebo-controlled trials. For men and all indications, the most common adverse reactions (>2% and twice placebo) included: ejaculation failure, decreased libido, erectile dysfunction, ejaculation disorder, and male sexual dysfunction. For women, the most common adverse reaction (≥2% and twice placebo) was decreased libido.

Table 4: Most Common Sexual Adverse Reactions (≥2% and twice placebo) in Men or Women from ZOLOFT Pooled Controlled Trials in Adults with MDD, OCD, PD, PTSD, SAD, and PMDD
 | ZOLOFT | Placebo
Men only | (N=1316) | (N=973)
Ejaculation failure | 8% | 1%
Libido decreased | 7% | 2%
Erectile dysfunction | 4% | 1%
Ejaculation disorder | 3% | 0%
Male sexual dysfunction | 2% | 0%
Women only | (N=1750) | (N=1320)
Libido decreased | 4% | 2%

Adverse Reactions in Pediatric Patients

In 281 pediatric patients treated with ZOLOFT in placebo-controlled studies, the overall profile of adverse reactions was generally similar to that seen in adult studies. Adverse reactions that do not appear in Table 3 (most common adverse reactions in adults) yet were reported in at least 2% of pediatric patients and at a rate of at least twice the placebo rate include fever, hyperkinesia, urinary incontinence, aggression, epistaxis, purpura, arthralgia, decreased weight, muscle twitching, and anxiety.

Other Adverse Reactions Observed During the Premarketing Evaluation of ZOLOFT

Other infrequent adverse reactions, not described elsewhere in the prescribing information, occurring at an incidence of < 2% in patients treated with ZOLOFT were:

Cardiac disorders - tachycardia

Ear and labyrinth disorders - tinnitus

Endocrine disorders - hypothyroidism

Eye disorders - mydriasis, blurred vision

Gastrointestinal disorders - hematochezia, melena, rectal hemorrhage

General disorders and administration site conditions - edema, gait disturbance, irritability, pyrexia

Hepatobiliary disorders - elevated liver enzymes

Immune system disorders - anaphylaxis

Metabolism and nutrition disorders - diabetes mellitus, hypercholesterolemia, hypoglycemia, increased appetite

Musculoskeletal and connective tissue disorders - arthralgia, muscle spasms, tightness, or twitching

Nervous system disorders - ataxia, coma, convulsion, decreased alertness, hypoesthesia, lethargy, psychomotor hyperactivity, syncope

Psychiatric disorders - aggression, bruxism, confusional state, euphoric mood, hallucination

Renal and urinary disorders - hematuria

Reproductive system and breast disorders - galactorrhea, priapism, vaginal hemorrhage

Respiratory, thoracic and mediastinal disorders - bronchospasm, epistaxis, yawning

Skin and subcutaneous tissue disorders - alopecia; cold sweat; dermatitis; dermatitis bullous; pruritus; purpura; erythematous, follicular, or maculopapular rash; urticaria

Vascular disorders - hemorrhage, hypertension, vasodilation

6.2 Post-marketing Experience

The following adverse reactions have been identified during postapproval use of ZOLOFT. Because these reactions are reported voluntarily from a population of uncertain size, it is not always possible to reliably estimate their frequency or establish a causal relationship to drug exposure.

Bleeding or clotting disorders - increased coagulation times (altered platelet function)

Cardiac disorders - AV block, bradycardia, atrial arrhythmias, QTc-interval prolongation, ventricular tachycardia (including Torsade de Pointes) [See Clinical Pharmacology (12.2)]

Endocrine disorders - gynecomastia, hyperprolactinemia, menstrual irregularities, SIADH

Eye disorders - blindness, optic neuritis, cataract

Hepatobiliary disorders - severe liver events (including hepatitis, jaundice, liver failure with some fatal outcomes), pancreatitis

Hemic and lymphatic disorders - agranulocytosis, aplastic anemia and pancytopenia, leukopenia, thrombocytopenia, lupus-like syndrome, serum sickness

Immune system disorders - angioedema

Metabolism and nutrition disorders - hyponatremia, hyperglycemia

Musculoskeletal and connective tissue disorders - rhabdomyolysis, trismus

Nervous system disorders - serotonin syndrome, extrapyramidal symptoms (including akathisia and dystonia), oculogyric crisis

Psychiatric disorders - psychosis, enuresis, paroniria

Renal and urinary disorders - acute renal failure

Respiratory, thoracic and mediastinal disorders - pulmonary hypertension, eosinophilic pneumonia, anosmia, hyposmia

Skin and subcutaneous tissue disorders - photosensitivity skin reaction and other severe cutaneous reactions, which potentially can be fatal, such as Stevens-Johnson Syndrome (SJS) and toxic epidermal necrolysis (TEN)

Vascular disorders - cerebrovascular spasm (including reversible cerebral vasoconstriction syndrome and Call‑Fleming syndrome), vasculitis

7 DRUG INTERACTIONS

7.1 Clinically Significant Drug Interactions

Table 5 includes clinically significant drug interactions with ZOLOFT [See Clinical Pharmacology (12.3)].

Table 5. Clinically-Significant Drug Interactions with ZOLOFT
Monoamine Oxidase Inhibitors (MAOIs)
Clinical Impact: | The concomitant use of SSRIs including ZOLOFT and MAOIs increases the risk of serotonin syndrome.
Intervention: | ZOLOFT is contraindicated in patients taking MAOIs, including MAOIs such as linezolid or intravenous methylene blue [See Dosage and Administration (2.5), Contraindications (4), Warnings and Precautions (5.2)].
Examples: | selegiline, tranylcypromine, isocarboxazid, phenelzine, linezolid, methylene blue
Pimozide
Clinical Impact: | Increased plasma concentrations of pimozide, a drug with a narrow therapeutic index, may increase the risk of QTc prolongation and ventricular arrhythmias.
Intervention: | Concomitant use of pimozide and ZOLOFT is contraindicated [See Contraindications (4)].
Other Serotonergic Drugs
Clinical Impact: | The concomitant use of serotonergic drugs with ZOLOFT increases the risk of serotonin syndrome.
Intervention: | Monitor patients for signs and symptoms of serotonin syndrome, particularly during treatment initiation and dosage increases. If serotonin syndrome occurs, consider discontinuation of ZOLOFT and/or concomitant serotonergic drugs [See Warnings and Precautions (5.2)].
Examples: | Other SSRIs, SNRIs, triptans, tricyclic antidepressants, opioids, lithium, tryptophan, buspirone, amphetamines, and St. John’s Wort.
Drugs that Interfere with Hemostasis (antiplatelet agents and anticoagulants)
Clinical Impact: | The concurrent use of an antiplatelet agent or anticoagulant with ZOLOFT may potentiate the risk of bleeding.
Intervention: | Inform patients of the increased risk of bleeding associated with the concomitant use of ZOLOFT and antiplatelet agents and anticoagulants. For patients taking warfarin, carefully monitor the international normalized ratio [See Warnings and Precautions (5.3)].
Examples: | aspirin, clopidogrel, heparin, warfarin
Drugs Highly Bound to Plasma Protein
Clinical Impact: | ZOLOFT is highly bound to plasma protein. The concomitant use of ZOLOFT with another drug that is highly bound to plasma protein may increase free concentrations of ZOLOFT or other tightly-bound drugs in plasma [See Clinical Pharmacology (12.3)].
Intervention: | Monitor for adverse reactions and reduce dosage of ZOLOFT or other protein-bound drugs as warranted.
Examples: | warfarin
Drugs Metabolized by CYP2D6
Clinical Impact: | ZOLOFT is a CYP2D6 inhibitor [See Clinical Pharmacology (12.3)]. The concomitant use of ZOLOFT with a CYP2D6 substrate may increase the exposure of the CYP2D6 substrate.
Intervention: | Decrease the dosage of a CYP2D6 substrate if needed with concomitant ZOLOFT use. Conversely, an increase in dosage of a CYP2D6 substrate may be needed if ZOLOFT is discontinued.
Examples: | propafenone, flecainide, atomoxetine, desipramine, dextromethorphan, metoprolol, nebivolol, perphenazine, thioridazine, tolterodine, venlafaxine
Phenytoin
Clinical Impact: | Phenytoin is a narrow therapeutic index drug. ZOLOFT may increase phenytoin concentrations.
Intervention: | Monitor phenytoin levels when initiating or titrating ZOLOFT. Reduce phenytoin dosage if needed.
Examples: | phenytoin, fosphenytoin
Drugs that Prolong the QTc Interval
Clinical Impact: | The risk of QTc prolongation and/or ventricular arrhythmias (e.g., TdP) is increased with concomitant use of other drugs which prolong the QTc interval [See Warnings and Precautions (5.10), Clinical Pharmacology (12.2)].
Intervention: | Pimozide is contraindicated for use with sertraline. Avoid the concomitant use of drugs known to prolong the QTc interval.
Examples: | Specific antipsychotics (e.g., ziprasidone, iloperidone, chlorpromazine, mesoridazine, droperidol); specific antibiotics (e.g., erythromycin, gatifloxacin, moxifloxacin, sparfloxacin); Class 1A antiarrhythmic medications (e.g., quinidine, procainamide); Class III antiarrhythmics (e.g., amiodarone, sotalol); and others (e.g., pentamidine, levomethadyl acetate, methadone, halofantrine, mefloquine, dolasetron mesylate, probucol or tacrolimus).

7.2 Drugs Having No Clinically Important Interactions with ZOLOFT

Based on pharmacokinetic studies, no dosage adjustment of ZOLOFT is necessary when used in combination with cimetidine. Additionally, no dosage adjustment is required for diazepam, lithium, atenolol, tolbutamide, digoxin, and drugs metabolized by CYP3A4, when ZOLOFT is administered concomitantly [See Clinical Pharmacology (12.3)].

7.3 False-Positive Screening Tests for Benzodiazepines

False-positive urine immunoassay screening tests for benzodiazepines have been reported in patients taking ZOLOFT. This finding is due to lack of specificity of the screening tests. False-positive test results may be expected for several days following discontinuation of ZOLOFT. Confirmatory tests, such as gas chromatography/mass spectrometry, will distinguish sertraline from benzodiazepines.

8 USE IN SPECIFIC POPULATIONS

8.1 Pregnancy

Pregnancy Exposure Registry

There is a pregnancy exposure registry that monitors pregnancy outcomes in women exposed to antidepressants during pregnancy. Healthcare providers should encourage patients to enroll by calling the National Pregnancy Registry for Antidepressants at 1-866-961-2388 or visiting online at https://womensmentalhealth.org/research/pregnancyregistry/antidepressants.

Risk Summary

Based on data from published observational studies, exposure to SSRIs, particularly in the month before delivery, has been associated with a less than 2-fold increase in the risk of postpartum hemorrhage [see Warnings and Precautions (5.3) and Clinical Considerations].

Overall, available published epidemiologic studies of pregnant women exposed to sertraline in the first trimester suggest no difference in major birth defect risk compared to the background rate for major birth defects in comparator populations. Some studies have reported increases for specific major birth defects; however, these study results are inconclusive [See Data]. There are clinical considerations regarding neonates exposed to SSRIs and SNRIs, including ZOLOFT, during the third trimester of pregnancy [See Clinical Considerations].

Although no teratogenicity was observed in animal reproduction studies, delayed fetal ossification was observed when sertraline was administered during the period of organogenesis at doses less than the maximum recommended human dose (MRHD) in rats and doses 3.1 times the MRHD in rabbits on a mg/m^2 basis in adolescents. When sertraline was administered to female rats during the last third of gestation, there was an increase in the number of stillborn pups and pup deaths during the first four days after birth at the MRHD [See Data].

The background risk of major birth defects and miscarriage for the indicated population are unknown. In the U.S. general population, the estimated background risk of major birth defects and miscarriage in clinically recognized pregnancies is 2-4% and 15-20%, respectively. Advise a pregnant woman of possible risks to the fetus when prescribing ZOLOFT.

ZOLOFT oral solution contains 12% alcohol and is not recommended during pregnancy because there is no known safe level of alcohol exposure during pregnancy.

Clinical Considerations

Disease-associated Maternal and/or Embryo/Fetal Risk

A prospective longitudinal study followed 201 pregnant women with a history of major depression who were euthymic taking antidepressants at the beginning of pregnancy. The women who discontinued antidepressants during pregnancy were more likely to experience a relapse of major depression than women who continued antidepressants. Consider the risks of untreated depression when discontinuing or changing treatment with antidepressant medication during pregnancy and postpartum.

Maternal Adverse Reactions

Use of ZOLOFT in the month before delivery may be associated with an increased risk of postpartum hemorrhage [see Warnings and Precautions (5.3)].

Fetal/Neonatal Adverse Reactions

Exposure to SSRIs and SNRIs, including ZOLOFT in late pregnancy may lead to an increased risk for neonatal complications requiring prolonged hospitalization, respiratory support, and tube feeding, and/or persistent pulmonary hypertension of the newborn (PPHN).

When treating a pregnant woman with ZOLOFT during the third trimester, carefully consider both the potential risks and benefits of treatment. Monitor neonates who were exposed to ZOLOFT in the third trimester of pregnancy for PPHN and drug discontinuation syndrome [See Data].

Data

Human Data

Third Trimester Exposure

Neonates exposed to ZOLOFT and other SSRIs or SNRIs late in the third trimester have developed complications requiring prolonged hospitalization, respiratory support, and tube feeding. These findings are based on post-marketing reports. Such complications can arise immediately upon delivery. Reported clinical findings have included respiratory distress, cyanosis, apnea, seizures, temperature instability, feeding difficulty, vomiting, hypoglycemia, hypotonia, hypertonia, hyperreflexia, tremor, jitteriness, irritability, and constant crying. These features are consistent with either a direct toxic effect of SSRIs and SNRIs or, possibly, a drug discontinuation syndrome. In some cases, the clinical picture was consistent with serotonin syndrome [See Warnings and Precautions (5.2)].

Exposure during late pregnancy to SSRIs may have an increased risk for persistent pulmonary hypertension of the newborn (PPHN). PPHN occurs in 1-2 per 1,000 live births in the general population and is associated with substantial neonatal morbidity and mortality. In a retrospective case-control study of 377 women whose infants were born with PPHN and 836 women whose infants were born healthy, the risk for developing PPHN was approximately six-fold higher for infants exposed to SSRIs after the 20th week of gestation compared to infants who had not been exposed to antidepressants during pregnancy. A study of 831,324 infants born in Sweden in 1997-2005 found a PPHN risk ratio of 2.4 (95% CI 1.2-4.3) associated with patient-reported maternal use of SSRIs “in early pregnancy” and a PPHN risk ratio of 3.6 (95% CI 1.2-8.3) associated with a combination of patient-reported maternal use of SSRIs “in early pregnancy” and an antenatal SSRI prescription “in later pregnancy”.

First Trimester Exposure

The weight of evidence from epidemiologic studies of pregnant women exposed to sertraline in the first trimester suggest no difference in major birth defect risk compared to the background rate for major birth defects in pregnant women who were not exposed to sertraline. A meta-analysis of studies suggest no increase in the risk of total malformations (summary odds ratio=1.01, 95% CI=0.88-1.17) or cardiac malformations (summary odds ratio=0.93, 95% CI=0.70-1.23) among offspring of women with first trimester exposure to sertraline. An increased risk of congenital cardiac defects, specifically septal defects, the most common type of congenital heart defect, was observed in some published epidemiologic studies with first trimester sertraline exposure; however, most of these studies were limited by the use of comparison populations that did not allow for the control of confounders such as the underlying depression and associated conditions and behaviors, which may be factors associated with increased risk of these malformations.

Animal Data

Reproduction studies have been performed in rats and rabbits at doses up to 80 mg/kg/day and 40 mg/kg/day, respectively. These doses correspond to approximately 3.1 times the maximum recommended human dose (MRHD) of 200 mg/day on a mg/m^2 basis in adolescents. There was no evidence of teratogenicity at any dose level. When pregnant rats and rabbits were given sertraline during the period of organogenesis, delayed ossification was observed in fetuses at doses of 10 mg/kg (0.4 times the MRHD on a mg/m2 basis) in rats and 40 mg/kg (3.1 times the MRHD on a mg/m^2 basis) in rabbits. When female rats received sertraline during the last third of gestation and throughout lactation, there was an increase in stillborn pups and pup deaths during the first 4 days after birth. Pup body weights were also decreased during the first four days after birth. These effects occurred at a dose of 20 mg/kg (0.8 times the MRHD on a mg/m^2 basis). The no effect dose for rat pup mortality was 10 mg/kg (0.4 times the MRHD on a mg/m^2 basis). The decrease in pup survival was shown to be due to in utero exposure to sertraline. The clinical significance of these effects is unknown.

8.2 Lactation

Risk Summary

Available data from published literature demonstrate low levels of sertraline and its metabolites in human milk [See Data]. There are no data on the effects of sertraline on milk production. The developmental and health benefits of breastfeeding should be considered along with the mother’s clinical need for ZOLOFT and any potential adverse effects on the breastfed infant from the drug or from the underlying maternal condition.

Data

In a published pooled analysis of 53 mother-infant pairs, exclusively human milk-fed infants had an average of 2% (range 0% to 15%) of the sertraline serum levels measured in their mothers. No adverse reactions were observed in these infants.

8.4 Pediatric Use

The safety and efficacy of ZOLOFT have been established in the treatment of OCD in pediatric patients aged 6 to 17 [See Adverse Reactions (6.1), Clinical Pharmacology (12.3), Clinical Studies (14.2)].

Safety and effectiveness in pediatric patients in patients with OCD below the age of 6 have not been established. Safety and effectiveness have not been established in pediatric patients for indications other than OCD.

Two placebo-controlled trials were conducted in pediatric patients with MDD, but the data were not sufficient to support an indication for use in pediatric patients.

Monitoring Pediatric Patients Treated with ZOLOFT

Monitor all patients being treated with antidepressants for clinical worsening, suicidal thoughts, and unusual changes in behavior, especially during the initial few months of treatment, or at times of dose increases or decreases [See Boxed Warning, Warnings and Precautions (5.1)]. Decreased appetite and weight loss have been observed with the use of SSRIs. Monitor weight and growth in pediatric patients treated with an SSRI such as ZOLOFT.

Weight Loss in Studies in Pediatric Patients with MDD

In a pooled analysis of two 10-week, double-blind, placebo-controlled, flexible dose (50-200 mg) outpatient trials for MDD (n=373), there was a difference in weight change between ZOLOFT and placebo of roughly 1 kg, for both children (ages 6-11) and adolescents (ages 12-17), in both age groups representing a slight weight loss for the ZOLOFT group compared to a slight gain for the placebo group. For children, about 7% of the ZOLOFT-treated patients had a weight loss greater than 7% of body weight compared to 0% of the placebo-treated patients; for adolescents, about 2% of ZOLOFT-treated patients had a weight loss > 7% of body weight compared to about 1% of placebo-treated patients.

A subset of patients who completed the randomized controlled trials in patients with MDD (ZOLOFT n=99, placebo n=122) were continued into a 24-week, flexible-dose, open-label, extension study. Those subjects who completed 34 weeks of ZOLOFT treatment (10 weeks in a placebo-controlled trial + 24 weeks open-label, n=68) had weight gain that was similar to that expected using data from age-adjusted peers. However, there are no studies that directly evaluate the long-term effects of ZOLOFT on the growth, development, and maturation in pediatric patients.

Alcohol Content in ZOLOFT Oral Solution

ZOLOFT oral solution contains 12% alcohol.

Juvenile Animal Data

A study conducted in juvenile rats at clinically relevant doses showed delay in sexual maturation, but there was no effect on fertility in either males or females.

In this study in which juvenile rats were treated with oral doses of sertraline at 0, 10, 40 or 80 mg/kg/day from postnatal day 21 to 56, a delay in sexual maturation was observed in males treated with 80 mg/kg/day and females treated with doses ≥10 mg/kg/day. There was no effect on male and female reproductive endpoints or neurobehavioral development up to the highest dose tested (80 mg/kg/day), except a decrease in auditory startle response in females at 40 and 80 mg/kg/day at the end of treatment but not at the end of the drug-free period. The highest dose of 80 mg/kg/day produced plasma levels (AUC) of sertraline 5 times those seen in pediatric patients (6-17 years of age) receiving the maximum recommended dose of sertraline (200 mg/day).

8.5 Geriatric Use

Of the total number of patients in clinical studies of ZOLOFT in patients with MDD, OCD, PD, PTSD, SAD and PMDD, 797 (17%) were ≥ 65 years old, while 197 (4%) were ≥ 75 years old.

No overall differences in safety or effectiveness were observed between these subjects and younger subjects, and other reported clinical experience has not identified differences in responses between the elderly and younger patients. In general, dose selection for an elderly patient should be conservative, usually starting at the low end of the dosing range, reflecting the greater frequency of decreased hepatic, renal, or cardiac function, and of concomitant disease or other drug therapy.

In 354 geriatric subjects treated with ZOLOFT in MDD placebo-controlled trials, the overall profile of adverse reactions was generally similar to that shown in Table 3 [See Adverse Reactions (6.1)], except for tinnitus, arthralgia with an incidence of at least 2% and at a rate greater than placebo in geriatric patients.

SNRIs and SSRIs, including ZOLOFT, have been associated with cases of clinically significant hyponatremia in elderly patients, who may be at greater risk for this adverse reaction [See Warnings and Precautions (5.8)].

8.6 Hepatic Impairment

The recommended dosage in patients with mild hepatic impairment (Child-Pugh score 5 or 6) is half the recommended dosage due to increased exposure in this patient population. The use of ZOLOFT in patients with moderate (Child-Pugh score 7 to 10) or severe hepatic impairment (Child-Pugh score 10-15) is not recommended, because ZOLOFT is extensively metabolized, and the effects of ZOLOFT in patients with moderate and severe hepatic impairment have not been studied [See Dosage and Administration (2.4), Clinical Pharmacology (12.3)].

8.7 Renal Impairment

No dose adjustment is needed in patients with mild to severe renal impairment. Sertraline exposure does not appear to be affected by renal impairment [See Clinical Pharmacology (12.3)].

9 DRUG ABUSE AND DEPENDENCE

9.1 Controlled Substance

ZOLOFT contains sertraline, which is not a controlled substance.

9.2 Abuse

In a placebo-controlled, double-blind, randomized study of the comparative abuse liability of ZOLOFT, alprazolam, and d-amphetamine in humans, ZOLOFT did not produce the positive subjective effects indicative of abuse potential, such as euphoria or drug liking, that were observed with the other two drugs.

10 OVERDOSAGE

The following have been reported with sertraline tablet overdosage:

- Seizures, which may be delayed, and altered mental status including coma.
- Cardiovascular toxicity, which may be delayed, including QRS and QTc interval prolongation. Hypertension most commonly seen, but rarely can see hypotension alone or with co-ingestants including alcohol.
- Serotonin syndrome (patients with a multiple drug overdosage with other proserotonergic drugs may have a higher risk).

Gastrointestinal decontamination with activated charcoal should be considered in patients who present early after a sertraline overdose. Consider contacting a Poison Center (1-800-221-2222) or a medical toxicologist for additional overdosage management recommendations.

11 DESCRIPTION

ZOLOFT contains sertraline hydrochloride, an SSRI. Sertraline hydrochloride has a molecular weight of 342.7 and has the following chemical name: (1S‑cis)‑4‑(3,4‑dichlorophenyl)‑1,2,3,4‑tetrahydro-N‑methyl‑1‑naphthalenamine hydrochloride. The empirical formula C17H17NCl2•HCl is represented by the following structural formula:

Sertraline hydrochloride is a white crystalline powder that is slightly soluble in water and isopropyl alcohol, and sparingly soluble in ethanol.

ZOLOFT tablets for oral administration contain 28.0 mg, 56.0 mg and 111.9 mg sertraline hydrochloride equivalent to 25, 50 and 100 mg of sertraline and the following inactive ingredients: dibasic calcium phosphate dihydrate, D & C Yellow #10 aluminum lake (in 25 mg tablet), FD & C Blue #1 aluminum lake (in 25 mg tablet), FD & C Red #40 aluminum lake (in 25 mg tablet), FD & C Blue #2 aluminum lake (in 50 mg tablet), hydroxypropyl cellulose, hypromellose, magnesium stearate, microcrystalline cellulose, polyethylene glycol, polysorbate 80, sodium starch glycolate, synthetic yellow iron oxide (in 100 mg tablet), and titanium dioxide.

ZOLOFT oral solution is available in a multidose 60 mL bottle. Each mL of solution contains 22.4 mg sertraline hydrochloride equivalent to 20 mg of sertraline. The solution contains the following inactive ingredients: glycerin, alcohol (12%), menthol, butylated hydroxytoluene (BHT). The oral solution must be diluted prior to administration [See Dosage and Administration (2.7)]. The dispenser contains dry natural rubber.

12 CLINICAL PHARMACOLOGY

12.1 Mechanism of Action

Sertraline potentiates serotonergic activity in the central nervous system through inhibition of neuronal reuptake of serotonin (5-HT).

12.2 Pharmacodynamics

Studies at clinically relevant doses have demonstrated that sertraline blocks the uptake of serotonin into human platelets. In vitro studies in animals also suggest that sertraline is a potent and selective inhibitor of neuronal serotonin reuptake and has only very weak effects on norepinephrine and dopamine neuronal reuptake. In vitro studies have shown that sertraline has no significant affinity for adrenergic (alpha1, alpha2, beta), cholinergic, GABA, dopaminergic, histaminergic, serotonergic (5HT1A, 5HT1B, 5HT2), or benzodiazepine receptors. The chronic administration of sertraline was found in animals to down regulate brain norepinephrine receptors. Sertraline does not inhibit monoamine oxidase.

Alcohol

In healthy subjects, the acute cognitive and psychomotor effects of alcohol were not potentiated by ZOLOFT.

Cardiac Electrophysiology

The effect of sertraline on the QTc interval was evaluated in a randomized, double-blind, placebo- and positive-controlled three-period crossover thorough QTc study in 54 healthy adult subjects. At 2-fold the maximum recommended daily dose (~3-fold the steady-state exposure for sertraline and N-desmethylsertraline), the largest mean ΔΔQTc was 10 ms with upper bound of two-sided 90% confidence interval of 12 ms. The length of the QTc interval was also positively correlated with serum concentrations of sertraline and N- desmethylsertraline concentrations. These concentration-based analyses, however, indicated a lesser effect on QTc at maximally observed concentration than in the primary analysis [See Warnings and Precautions (5), Adverse Reactions (6), Drug Interactions (7), Overdosage (10)].

12.3 Pharmacokinetics

Absorption

Following oral once-daily ZOLOFT dosing over the range of 50 to 200 mg for 14 days, mean peak plasma concentrations (Cmax) of sertraline occurred between 4.5 to 8.4 hours post-dosing. The average terminal elimination half-life of plasma sertraline is about 26 hours. Consistent with the terminal elimination half-life, there is an approximately two-fold accumulation up to steady-state concentrations, which are achieved after one week of once-daily dosing. Linear dose-proportional pharmacokinetics were demonstrated in a single dose study in which the Cmax and area under the plasma concentration time curve (AUC) of sertraline were proportional to dose over a range of 50 to 200 mg. The single dose bioavailability of ZOLOFT tablets is approximately equal to an equivalent dose of ZOLOFT oral solution. Administration with food causes a small increase in Cmax and AUC.

Metabolism

Sertraline undergoes extensive first pass metabolism. The principal initial pathway of metabolism for sertraline is N‑demethylation. N‑desmethylsertraline has a plasma terminal elimination half‑life of 62 to 104 hours. Both in vitro biochemical and in vivo pharmacological testing have shown N‑desmethylsertraline to be substantially less active than sertraline. Both sertraline and N‑desmethylsertraline undergo oxidative deamination and subsequent reduction, hydroxylation, and glucuronide conjugation. In a study of radiolabeled sertraline involving two healthy male subjects, sertraline accounted for less than 5% of the plasma radioactivity. About 40‑45% of the administered radioactivity was recovered in urine in 9 days. Unchanged sertraline was not detectable in the urine. For the same period, about 40‑45% of the administered radioactivity was accounted for in feces, including 12‑14% unchanged sertraline.

Desmethylsertraline exhibits time‑related, dose dependent increases in AUC (0‑24-hour), Cmax and Cmin, with about a 5‑ to 9-fold increase in these pharmacokinetic parameters between day 1 and day 14.

Protein Binding

In vitro protein binding studies performed with radiolabeled 3H-sertraline showed that sertraline is highly bound to serum proteins (98%) in the range of 20 to 500 ng/mL. However, at up to 300 and 200 ng/mL concentrations, respectively, sertraline and N-desmethylsertraline did not alter the plasma protein binding of two other highly protein bound drugs, warfarin and propranolol.

Studies in Specific Populations

Pediatric Patients

Sertraline pharmacokinetics were evaluated in a group of 61 pediatric patients (29 aged 6-12 years, 32 aged 13-17 years) including both males (N=28) and females (N=33). Relative to the adults, pediatric patients aged 6-12 years and 13-17 years showed about 22% lower AUC (0-24 hr) and Cmax values when plasma concentration was adjusted for weight. The half-life was similar to that in adults, and no gender-associated differences were observed [See Dosage and Administration (2.1), Use in Specific Populations (8.4)].

Geriatric Patients

Sertraline plasma clearance in a group of 16 (8 male, 8 female) elderly patients treated with 100 mg/day of ZOLOFT for 14 days was approximately 40% lower than in a similarly studied group of younger (25 to 32 year old) individuals. Steady-state, therefore, was achieved after 2 to 3 weeks in older patients. The same study showed a decreased clearance of desmethylsertraline in older males, but not in older females [See Use in Specific Populations (8.5)].

Hepatic Impairment

In patients with chronic mild liver impairment (N=10: 8 patients with Child-Pugh scores of 5-6; and 2 patients with Child-Pugh scores of 7-8) who received 50 mg of ZOLOFT per day for 21 days, sertraline clearance was reduced, resulting in approximately 3-fold greater exposure compared to age-matched volunteers with normal hepatic function (N=10). The exposure to desmethylsertraline was approximately 2-fold greater in patients with mild hepatic impairment compared to age-matched volunteers with normal hepatic function. There were no significant differences in plasma protein binding observed between the two groups. The effects of ZOLOFT in patients with moderate and severe hepatic impairment have not been studied [See Dosage and Administration (2.4), Use in Specific Populations (8.6)].

Renal Impairment

Sertraline is extensively metabolized and excretion of unchanged drug in urine is a minor route of elimination. In volunteers with mild to moderate (CLcr=30-60 mL/min), moderate to severe (CLcr=10-29 mL/min) or severe (receiving hemodialysis) renal impairment (N=10 each group), the pharmacokinetics and protein binding of 200 mg sertraline per day maintained for 21 days were not altered compared to age-matched volunteers (N=12) with no renal impairment. Thus sertraline multiple dose pharmacokinetics appear to be unaffected by renal impairment [See Use in Specific Populations (8.7)].

Drug Interaction Studies

Pimozide

In a controlled study of a single dose (2 mg) of pimozide, 200 mg ZOLOFT (once daily) co-administration to steady state was associated with a mean increase in pimozide AUC and Cmax of about 40%, but was not associated with any changes in ECG. The highest recommended pimozide dose (10 mg) has not been evaluated in combination with ZOLOFT. The effect on QTc interval and PK parameters at doses higher than 2 mg of pimozide are not known [See Drug Interactions (7.1)].

Drugs Metabolized by CYP2D6

Many antidepressant drugs (e.g., SSRIs, including ZOLOFT, and most tricyclic antidepressant drugs) inhibit the biochemical activity of the drug metabolizing isozyme CYP2D6 (debrisoquin hydroxylase), and, thus, may increase the plasma concentrations of co-administered drugs that are metabolized by CYP2D6. The drugs for which this potential interaction is of greatest concern are those metabolized primarily by CYP2D6 and that have a narrow therapeutic index (e.g., tricyclic antidepressant drugs and the Type 1C antiarrhythmics propafenone and flecainide). The extent to which this interaction is an important clinical problem depends on the extent of the inhibition of CYP2D6 by the antidepressant and the therapeutic index of the co-administered drug. There is variability among the drugs effective in the treatment of MDD in the extent of clinically important 2D6 inhibition, and in fact ZOLOFT at lower doses has a less prominent inhibitory effect on 2D6 than some others in the class. Nevertheless, even ZOLOFT has the potential for clinically important 2D6 inhibition [See Drug Interactions (7.1)].

Phenytoin

Clinical trial data suggested that ZOLOFT may increase phenytoin concentrations [See Drug Interactions (7.1)].

Cimetidine

In a study assessing disposition of ZOLOFT (100 mg) on the second of 8 days of cimetidine administration (800 mg daily), there were increases in ZOLOFT mean AUC (50%), Cmax (24%) and half-life (26%) compared to the placebo group [See Drug Interactions (7.2)].

Diazepam

In a study comparing the disposition of intravenously administered diazepam before and after 21 days of dosing with either ZOLOFT (50 to 200 mg/day escalating dose) or placebo, there was a 32% decrease relative to baseline in diazepam clearance for the ZOLOFT group compared to a 19% decrease relative to baseline for the placebo group (p<0.03). There was a 23% increase in Tmax for desmethyldiazepam in the ZOLOFT group compared to a 20% decrease in the placebo group (p<0.03) [See Drug Interactions (7.2)].

Lithium

In a placebo-controlled trial in normal volunteers, the administration of two doses of ZOLOFT did not significantly alter steady-state lithium levels or the renal clearance of lithium [See Drug Interactions (7.2)].

Tolbutamide

In a placebo-controlled trial in normal volunteers, administration of ZOLOFT for 22 days (including 200 mg/day for the final 13 days) caused a statistically significant 16% decrease from baseline in the clearance of tolbutamide following an intravenous 1000 mg dose. ZOLOFT administration did not noticeably change either the plasma protein binding or the apparent volume of distribution of tolbutamide, suggesting that the decreased clearance was due to a change in the metabolism of the drug [See Drug Interactions (7.2)].

Atenolol

ZOLOFT (100 mg) when administered to 10 healthy male subjects had no effect on the beta-adrenergic blocking ability of atenolol [See Drug Interactions (7.2)].

Digoxin

In a placebo-controlled trial in normal volunteers, administration of ZOLOFT for 17 days (including 200 mg/day for the last 10 days) did not change serum digoxin levels or digoxin renal clearance [See Drug Interactions (7.2)].

Drugs Metabolized by CYP3A4

In three separate in vivo interaction studies, ZOLOFT was co-administered with CYP3A4 substrates, terfenadine, carbamazepine, or cisapride under steady-state conditions. The results of these studies indicated that ZOLOFT did not increase plasma concentrations of terfenadine, carbamazepine, or cisapride. These data indicate that ZOLOFT’s extent of inhibition of CYP3A4 activity is not likely to be of clinical significance. Results of the interaction study with cisapride indicate that ZOLOFT 200 mg (once daily) induces the metabolism of cisapride (cisapride AUC and Cmax were reduced by about 35%) [See Drug Interactions (7.2)].

Microsomal Enzyme Induction

Preclinical studies have shown ZOLOFT to induce hepatic microsomal enzymes. In clinical studies, ZOLOFT was shown to induce hepatic enzymes minimally as determined by a small (5%) but statistically significant decrease in antipyrine half-life following administration of 200 mg of ZOLOFT per day for 21 days. This small change in antipyrine half-life reflects a clinically insignificant change in hepatic metabolism.

13 NONCLINICAL TOXICOLOGY

13.1 Carcinogenesis, Mutagenesis, Impairment of Fertility

Carcinogenesis

Lifetime carcinogenicity studies were carried out in CD-1 mice and Long-Evans rats at doses up to 40 mg/kg/day. These doses correspond to 1 times (mice) and 2 times (rats) the maximum recommended human dose (MRHD) of 200 mg/day on a mg/m^2 basis. There was a dose-related increase of liver adenomas in male mice receiving sertraline at 10-40 mg/kg (0.25-1.0 times the MRHD on a mg/m^2 basis). No increase was seen in female mice or in rats of either sex receiving the same treatments, nor was there an increase in hepatocellular carcinomas. Liver adenomas have a variable rate of spontaneous occurrence in the CD-1 mouse and are of unknown significance to humans. There was an increase in follicular adenomas of the thyroid in female rats receiving sertraline at 40 mg/kg (2 times the MRHD on a mg/m^2 basis); this was not accompanied by thyroid hyperplasia. While there was an increase in uterine adenocarcinomas in rats receiving sertraline at 10-40 mg/kg (0.5-2.0 times the MRHD on a mg/m^2 basis) compared to placebo controls, this effect was not clearly drug related.

Mutagenesis

Sertraline had no genotoxic effects, with or without metabolic activation, based on the following assays: bacterial mutation assay; mouse lymphoma mutation assay; and tests for cytogenetic aberrations in vivo in mouse bone marrow and in vitro in human lymphocytes.

Impairment of Fertility

A decrease in fertility was seen in one of two rat studies at a dose of 80 mg/kg (3.1 times the maximum recommended human dose on a mg/m^2 basis in adolescents).

14 CLINICAL STUDIES

Efficacy of ZOLOFT was established in the following trials:

- MDD: two short-term trials and one maintenance trials in adults [See Clinical Studies (14.1)].
- OCD: three short-term trials in adults and one short-term trial in pediatric patients [See Clinical Studies (14.2)].
- PD: three short-term trials and one maintenance trial in adults [See Clinical Studies (14.3)].
- PTSD: two short-term trials and one maintenance trial in adults [See Clinical Studies (14.4)].
- SAD: two short-term trials and one maintenance trial in adults [See Clinical Studies (14.5)].
- PMDD: two short-term trials in adult female patients [See Clinical Studies (14.6)].

14.1 Major Depressive Disorder

The efficacy of ZOLOFT as a treatment for MDD was established in two randomized, double-blind, placebo-controlled studies and one double-blind, randomized-withdrawal study following an open label study in adult (ages 18 to 65) outpatients who met the Diagnostic and Statistical Manual of Mental Disorders (DSM-III) criteria for MDD (studies MDD-1 and MDD-2).

- Study MDD-1 was an 8-week, 3-arm study with flexible dosing of ZOLOFT, amitriptyline, and placebo. Adult patients received ZOLOFT (N=126, in a daily dose titrated weekly to 50 mg, 100 mg, or 200 mg), amitriptyline (N=123, in a daily dose titrated weekly to 50 mg, 100 mg, or 150 mg), or placebo (N= 130).
- Study MDD-2 was a 6-week, multicenter parallel study of three fixed doses of ZOLOFT administered once daily at 50 mg (N=82), 100 mg (N=75), and 200 mg (N=56) doses and placebo (N=76) in the treatment of adult outpatients with MDD.

Overall, these studies demonstrated ZOLOFT to be superior to placebo on the Hamilton Rating Scale for Depression (HAMD-17) and the Clinical Global Impression Severity (CGI-S) of Illness and Global Improvement (CGI-I) scores. Study MDD-2 was not readily interpretable regarding a dose response relationship for effectiveness.

A third study (Study MDD-3) involved adult outpatients meeting the DSM-III criteria for MDD who had responded by the end of an initial 8-week open treatment phase on ZOLOFT 50-200 mg/day. These patients (n=295) were randomized to continuation on double-blind ZOLOFT 50-200 mg/day or placebo for 44 weeks. A statistically significantly lower relapse rate was observed for patients taking ZOLOFT compared to those on placebo: ZOLOFT [n=11 (8%)] and placebo [n=31 (39%)]. The mean ZOLOFT dose for completers was 70 mg/day.

Analyses for gender effects on outcome did not suggest any differential responsiveness on the basis of sex.

14.2 Obsessive-Compulsive Disorder

Adults with OCD

The effectiveness of ZOLOFT in the treatment of OCD was demonstrated in three multicenter placebo-controlled studies of adult (age 18-65) non-depressed outpatients (Studies OCD-1, OCD-2, and OCD-3). Patients in all three studies had moderate to severe OCD (DSM-III or DSM-III-R) with mean baseline ratings on the Yale-Brown Obsessive-Compulsive Scale (Y-BOCS) total score ranging from 23 to 25.

- Study OCD-1 was an 8-week randomized, placebo-controlled study with flexible dosing of ZOLOFT in a range of 50 to 200 mg/day, titrated in 50 mg increments every 4 days to a maximally tolerated dose; the mean dose for completers was 186 mg/day. Patients receiving ZOLOFT (N=43) experienced a mean reduction of approximately 4 points on the Y-BOCS total score which was statistically significantly greater than the mean reduction of 2 points in placebo-treated patients (N=44). The mean change in Y-BOCS from baseline to last visit (the primary efficacy endpoint) was -3.79 (ZOLOFT) and -1.48 (placebo).
- Study OCD-2 was a 12-week randomized, placebo-controlled fixed-dose study, including ZOLOFT doses of 50, 100, and 200 mg/day. ZOLOFT (N=240) was titrated to the assigned dose over two weeks in 50 mg increments every 4 days. Patients receiving ZOLOFT doses of 50 and 200 mg/day experienced mean reductions of approximately 6 points on the Y-BOCS total score, which were statistically significantly greater than the approximately 3 point reduction in placebo-treated patients (N=84). The mean change in Y-BOCS from baseline to last visit (the primary efficacy endpoint) was -5.7 (pooled results from ZOLOFT 50 mg, 100 mg, and 150 mg) and -2.85 (placebo).
- Study OCD-3 was a 12-week randomized, placebo controlled study with flexible dosing of ZOLOFT in a range of 50 to 200 mg/day; the mean dose for completers was 185 mg/day. ZOLOFT (N=241) was titrated to the assigned dose over two weeks in 50 mg increments every 4 days. Patients receiving ZOLOFT experienced a mean reduction of approximately 7 points on the Y-BOCS total score which was statistically significantly greater than the mean reduction of approximately 4 points in placebo-treated patients (N=84). The mean change in Y-BOCS from baseline to last visit (the primary efficacy endpoint) was - 6.5 (ZOLOFT) and -3.6 (placebo).

Analyses for age and gender effects on outcome did not suggest any differential responsiveness on the basis of age or sex.

The effectiveness of ZOLOFT was studied in the risk reduction of OCD relapse. In Study OCD-4, patients ranging in age from 18–79 meeting DSM-III-R criteria for OCD who had responded during a 52-week single-blind trial on ZOLOFT 50-200 mg/day (n=224) were randomized to continuation of ZOLOFT or to substitution of placebo for up to 28 weeks of observation for analysis of discontinuation due to relapse or insufficient clinical response. Response during the single-blind phase was defined as a decrease in the Y-BOCS score of ≥ 25% compared to baseline and a CGI-I of 1 (very much improved), 2 (much improved) or 3 (minimally improved). Insufficient clinical response during the double-blind phase indicated a worsening of the patient’s condition that resulted in study discontinuation, as assessed by the investigator. Relapse during the double-blind phase was defined as the following conditions being met (on three consecutive visits for 1 and 2, and condition 3 being met at visit 3):

- Condition 1: Y-BOCS score increased by ≥ 5 points, to a minimum of 20, relative to baseline;
- Condition 2: CGI-I increased by ≥ one point; and
- Condition 3: Worsening of the patient’s condition in the investigator’s judgment, to justify alternative treatment.

Patients receiving continued ZOLOFT treatment experienced a statistically significantly lower rate of discontinuation due to relapse or insufficient clinical response over the subsequent 28 weeks compared to those receiving placebo. This pattern was demonstrated in male and female subjects.

Pediatric Patients with OCD

The effectiveness of ZOLOFT for the treatment of OCD was demonstrated in a 12‑week, multicenter, placebo-controlled, parallel group study in a pediatric outpatient population (ages 6-17) (Study OCD-5). ZOLOFT (N=92) was initiated at doses of either 25 mg/day (pediatric patients ages 6-12) or 50 mg/day (adolescents, ages 13-17), and then titrated at 3 and 4 day intervals (25 mg incremental dose for pediatric patients ages 6‑12) or 1 week intervals (50 mg incremental dose adolescents ages 13-17) over the next four weeks to a maximum dose of 200 mg/day, as tolerated. The mean dose for completers was 178 mg/day. Dosing was once a day in the morning or evening. Patients in this study had moderate to severe OCD (DSM‑III‑R) with mean baseline ratings on the Children’s Yale‑Brown Obsessive‑Compulsive Scale (CY-BOCS) total score of 22. Patients receiving ZOLOFT experienced a mean reduction of approximately 7 units on the CY-BOCS total score which was statistically significantly greater than the 3 unit reduction for placebo patients (n=95). Analyses for age and gender effects on outcome did not suggest any differential responsiveness on the basis of age or sex.

14.3 Panic Disorder

The effectiveness of ZOLOFT in the treatment of PD was demonstrated in three double‑blind, placebo‑controlled studies (Studies PD-1, PD-2, and PD‑3) of adult outpatients who had a primary diagnosis of PD (DSM‑III‑R), with or without agoraphobia.

- Studies PD-1 and PD-2 were 10-week flexible dose studies of ZOLOFT (N=80 study PD-1 and N=88 study PD-2) compared to placebo (N=176 study PD-1 and PD-2). In both studies, ZOLOFT was initiated at 25 mg/day for the first week, then titrated in weekly increments of 50 mg per day to a maximum dose of 200 mg/day on the basis of clinical response and toleration. The mean ZOLOFT doses for completers to 10 weeks were 131 mg/day and 144 mg/day, respectively, for Studies PD-1 and PD-2. In these studies, ZOLOFT was shown to be statistically significantly more effective than placebo on change from baseline in panic attack frequency and on the Clinical Global Impression Severity (CGI-S) of Illness and Global Improvement (CGI-I) scores. The difference between ZOLOFT and placebo in reduction from baseline in the number of full panic attacks was approximately 2 panic attacks per week in both studies.
- Study PD-3 was a 12-week randomized, double-blind fixed-dose study, including ZOLOFT doses of 50, 100, and 200 mg/day. Patients receiving ZOLOFT (50 mg N=43, 100 mg N=44, 200 mg N=45) experienced a statistically significantly greater reduction in panic attack frequency than patients receiving placebo (N=45). Study PD-3 was not readily interpretable regarding a dose response relationship for effectiveness.

Subgroup analyses did not indicate that there were any differences in treatment outcomes as a function of age, race, or gender.

In Study PD-4, patients meeting DSM-III-R criteria for PD who had responded during a 52-week open trial on ZOLOFT 50-200 mg/day (n=183) were randomized to continuation of ZOLOFT or to substitution of placebo for up to 28 weeks of observation for discontinuation due to relapse or insufficient clinical response. Response during the open phase was defined as a CGI-I score of 1(very much improved) or 2 (much improved). Insufficient clinical response in the double-blind phase indicated a worsening of the patient’s condition that resulted in study discontinuation, as assessed by the investigator. Relapse during the double-blind phase was defined as the following conditions being met on three consecutive visits:

(1) CGI-I ≥ 3;

(2) meets DSM-III-R criteria for PD;

(3) number of panic attacks greater than at baseline.

Patients receiving continued ZOLOFT treatment experienced a statistically significantly lower rate of discontinuation due to relapse or insufficient clinical response over the subsequent 28 weeks compared to those receiving placebo. This pattern was demonstrated in male and female subjects.

14.4 Posttraumatic Stress Disorder

The effectiveness of ZOLOFT in the treatment of PTSD was established in two multicenter placebo‑controlled studies (Studies PSTD-1 and PSTD-2) of adult outpatients who met DSM‑III‑R criteria for PTSD. The mean duration of PTSD for these patients was 12 years (Studies PSTD-1 and PSTD-2 combined) and 44% of patients (169 of the 385 patients treated) had secondary depressive disorder.

Studies PSTD-1 and PSTD-2 were 12‑week flexible dose studies. ZOLOFT was initiated at 25 mg/day for the first week, and titrated in weekly increments of 50 mg per day to a maximum dose of 200 mg/day on the basis of clinical response and tolerability. The mean ZOLOFT dose for completers was 146 mg/day and 151 mg/day, respectively, for Studies PSTD-1 and PSTD-2. Study outcome was assessed by the Clinician‑Administered PTSD Scale Part 2 (CAPS), which is a multi‑item instrument that measures the three PTSD diagnostic symptom clusters of reexperiencing/intrusion, avoidance/numbing, and hyperarousal as well as the patient‑rated Impact of Event Scale (IES), which measures intrusion and avoidance symptoms. Patients receiving ZOLOFT (N=99 and N=94, respectively) showed statistically significant improvement compared to placebo (N=83 and N=92) on change from baseline to endpoint on the CAPS, IES, and on the Clinical Global Impressions (CGI-S) Severity of Illness and Global Improvement (CGI-I) scores.

In two additional placebo-controlled PTSD trials (Studies PSTD-3 and PSTD-4), the difference in response to treatment between patients receiving ZOLOFT and patients receiving placebo was not statistically significant. One of these additional studies was conducted in patients similar to those recruited for Studies PSTD-1 and PSTD-2, while the second additional study was conducted in predominantly male veterans.

As PTSD is a more common disorder in women than men, the majority (76%) of patients in Studies PSTD-1 and PSTD-2 described above were women. Post hoc exploratory analyses revealed a statistically significant difference between ZOLOFT and placebo on the CAPS, IES and CGI in women, regardless of baseline diagnosis of comorbid major depressive disorder, but essentially no effect in the relatively smaller number of men in these studies. The clinical significance of this apparent gender effect is unknown at this time. There was insufficient information to determine the effect of race or age on outcome.

In Study PSTD-5, patients meeting DSM-III-R criteria for PTSD who had responded during a 24-week open trial on ZOLOFT 50-200 mg/day (n=96) were randomized to continuation of ZOLOFT or to substitution of placebo for up to 28 weeks of observation for relapse. Response during the open phase was defined as a CGI-I of 1 (very much improved) or 2 (much improved), and a decrease in the CAPS-2 score of > 30% compared to baseline. Relapse during the double-blind phase was defined as the following conditions being met on two consecutive visits:

(1) CGI-I ≥ 3;

(2) CAPS-2 score increased by ≥ 30% and by ≥ 15 points relative to baseline; and

(3) worsening of the patient's condition in the investigator's judgment.

Patients receiving continued ZOLOFT treatment experienced statistically significantly lower relapse rates over the subsequent 28 weeks compared to those receiving placebo. This pattern was demonstrated in male and female subjects.

14.5 Social Anxiety Disorder

The effectiveness of ZOLOFT in the treatment of SAD (also known as social phobia) was established in two multicenter, randomized, placebo-controlled studies (Study SAD-1 and SAD-2) of adult outpatients who met DSM-IV criteria for SAD.

Study SAD-1 was a 12-week, flexible dose study comparing ZOLOFT (50-200 mg/day), n=211, to placebo, n=204, in which ZOLOFT was initiated at 25 mg/day for the first week, then titrated to the maximum tolerated dose in 50 mg increments biweekly. Study outcomes were assessed by the:

(1) Liebowitz Social Anxiety Scale (LSAS), a 24-item clinician administered instrument that measures fear, anxiety, and avoidance of social and performance situations, and

(2) Proportion of responders as defined by the Clinical Global Impression of Improvement (CGI-I) criterion of CGI-I ≤ 2 (very much or much improved).

ZOLOFT was statistically significantly more effective than placebo as measured by the LSAS and the percentage of responders.

Study SAD-2 was a 20-week, flexible dose study that compared ZOLOFT (50-200 mg/day), n=135, to placebo, n=69. ZOLOFT was titrated to the maximum tolerated dose in 50 mg increments every 3 weeks. Study outcome was assessed by the:

(1) Duke Brief Social Phobia Scale (BSPS), a multi-item clinician-rated instrument that measures fear, avoidance and physiologic response to social or performance situations,

(2) Marks Fear Questionnaire Social Phobia Subscale (FQ-SPS), a 5-item patient-rated instrument that measures change in the severity of phobic avoidance and distress, and

(3) CGI-I responder criterion of ≤ 2.

ZOLOFT was shown to be statistically significantly more effective than placebo as measured by the BSPS total score and fear, avoidance and physiologic factor scores, as well as the FQ-SPS total score, and to have statistically significantly more responders than placebo as defined by the CGI-I. Subgroup analyses did not suggest differences in treatment outcome on the basis of gender. There was insufficient information to determine the effect of race or age on outcome.

In Study SAD-3, patients meeting DSM-IV criteria for SAD who had responded while assigned to ZOLOFT (CGI-I of 1 or 2) during a 20-week placebo-controlled trial on ZOLOFT 50-200 mg/day were randomized to continuation of ZOLOFT or to substitution of placebo for up to 24 weeks of observation for relapse. Relapse was defined as ≥ 2 point increase in the Clinical Global Impression Severity of Illness (CGI-S) score compared to baseline or study discontinuation due to lack of efficacy. Patients receiving ZOLOFT continuation treatment experienced a statistically significantly lower relapse rate during this 24-week period than patients randomized to placebo substitution.

14.6 Premenstrual Dysphoric Disorder

The effectiveness of ZOLOFT for the treatment of PMDD was established in two double-blind, parallel group, placebo-controlled flexible dose trials (Studies PMDD-1 and PMDD-2) conducted over 3 menstrual cycles in adult female patients. The effectiveness of ZOLOFT for PMDD for more than 3 menstrual cycles has not been systematically evaluated in controlled trials.

Patients in Study PMDD-1 met DSM-III-R criteria for Late Luteal Phase Dysphoric Disorder (LLPDD), the clinical entity referred to as PMDD in DSM-IV. Patients in Study PMDD-2 met DSM-IV criteria for PMDD. Study PMDD-1 utilized continuous daily dosing throughout the study, while Study PMDD-2 utilized luteal phase dosing (intermittent dosing) for the 2 weeks prior to the onset of menses. The mean duration of PMDD symptoms was approximately 10.5 years in both studies. Patients taking oral contraceptives were excluded from these trials; therefore, the efficacy of ZOLOFT in combination with oral contraceptives for the treatment of PMDD is unknown.

Efficacy was assessed with the Daily Record of Severity of Problems (DRSP), a patient-rated instrument that mirrors the diagnostic criteria for PMDD as identified in the DSM-IV, and includes assessments for mood, physical symptoms, and other symptoms. Other efficacy assessments included the Hamilton Rating Scale for Depression (HAMD-17), and the Clinical Global Impression Severity of Illness (CGI-S) and Improvement (CGI-I) scores.

- In Study PMDD-1, involving 251 randomized patients, (n=125 on ZOLOFT and n=126 on placebo), ZOLOFT treatment was initiated at 50 mg/day and administered daily throughout the menstrual cycle. In subsequent cycles, ZOLOFT was titrated in 50 mg increments at the beginning of each menstrual cycle up to a maximum of 150 mg/day on the basis of clinical response and tolerability. The mean dose for completers was 102 mg/day. ZOLOFT administered daily throughout the menstrual cycle was statistically significantly more effective than placebo on change from baseline to endpoint on the DRSP total score, the HAMD-17 total score, and the CGI-S score, as well as the CGI-I score at endpoint.
- In Study PMDD-2, involving 281 randomized patients, (n=142 on ZOLOFT and n=139 on placebo), ZOLOFT treatment was initiated at 50 mg/day in the late luteal phase (last 2 weeks) of each menstrual cycle and then discontinued at the onset of menses (intermittent dosing). In subsequent cycles, patients were dosed in the range of 50-100 mg/day in the luteal phase of each cycle, on the basis of clinical response and tolerability. Patients who received 100 mg/day started with 50 mg/day for the first 3 days of the cycle, then 100 mg/day for the remainder of the cycle. The mean ZOLOFT dose for completers was 74 mg/day. ZOLOFT administered in the late luteal phase of the menstrual cycle was statistically significantly more effective than placebo on change from baseline to endpoint on the DRSP total score and the CGI-S score, as well as the CGI-I score at endpoint (Week 12).

There was insufficient information to determine the effect of race or age on outcome in these studies.

16 HOW SUPPLIED/STORAGE AND HANDLING

ZOLOFT 25 mg tablets: light green, film-coated, capsular-shaped tablets engraved on one side with “ZOLOFT” and on the other side scored and engraved with “25 mg”

NDC 58151-574-93 Bottles of 30

ZOLOFT 50 mg tablets: light blue, film-coated, capsular-shaped tablets engraved on one side with “ZOLOFT” and on the other side scored and engraved with “50 mg”

NDC 58151-575-93 Bottles of 30

NDC 58151-575-88 Unit Dose Packages of 100

ZOLOFT 100 mg tablets: light yellow, film-coated, capsular-shaped, tablets engraved on one side with “ZOLOFT” and on the other side scored and engraved with “100 mg”

NDC 58151-576-93 Bottles of 30

NDC 58151-576-88 Unit Dose Packages of 100

ZOLOFT oral solution: clear, colorless solution with a menthol scent containing sertraline hydrochloride equivalent to 20 mg of sertraline per mL and 12% alcohol

NDC 58151-601-35 Bottles containing 60 mL, each with an accompanying calibrated dropper that has 25 mg and 50 mg graduation marks.

Store ZOLOFT at 20°C to 25°C (68°F to 77°F); excursions permitted to 15°C to 30°C (59°F to 86°F) [See USP Controlled Room Temperature].

17 PATIENT COUNSELING INFORMATION

Advise the patient to read the FDA-approved patient labeling (Medication Guide).

Suicidal Thoughts and Behaviors

Advise patients and caregivers to look for the emergence of suicidality, especially early during treatment and when the dosage is adjusted up or down, and instruct them to report such symptoms to the healthcare provider [See Boxed Warning and Warnings and Precautions (5.1)].

Important Administration Instructions for Oral Solution

For patients prescribed ZOLOFT oral solution, inform them that:

- ZOLOFT oral solution must be diluted before use. Do not mix in advance.
- Use the dropper provided to remove the required amount of ZOLOFT oral solution and mix with 4 ounces (1/2 cup) of water, ginger ale, lemon/lime soda, lemonade or orange juice ONLY. Do not mix ZOLOFT oral solution with anything other than the liquids listed.
- Take the dose immediately after mixing. At times, a slight haze may appear after mixing; this is normal.
- The dropper dispenser contains dry natural rubber, a consideration for patients with latex sensitivity.

Disulfiram Contraindication for ZOLOFT Oral Solution

Inform patients not to take disulfiram when taking ZOLOFT oral solution. Concomitant use is contraindicated due the alcohol content of the oral solution [See Contraindication (4)].

Serotonin Syndrome

Caution patients about the risk of serotonin syndrome, particularly with the concomitant use of ZOLOFT with other serotonergic drugs including triptans, tricyclic antidepressants, opioids, lithium, tryptophan, buspirone, amphetamines, St. John’s Wort, and with drugs that impair metabolism of serotonin (in particular, MAOIs, both those intended to treat psychiatric disorders and also others, such as linezolid). Patients should contact their health care provider or report to the emergency room if they experience signs or symptoms of serotonin syndrome [See Warnings and Precautions (5.2), Drug Interactions (7.1)].

Increased Risk of Bleeding

Inform patients about the concomitant use of ZOLOFT with aspirin, NSAIDs, other antiplatelet drugs, warfarin, or other anticoagulants because the combined use has been associated with an increased risk of bleeding. Advise patients to inform their health care providers if they are taking or planning to take any prescription or over-the-counter medications that increase the risk of bleeding [See Warnings and Precautions (5.3)].

Activation of Mania/Hypomania

Advise patients and their caregivers to observe for signs of activation of mania/hypomania and instruct them to report such symptoms to the healthcare provider [See Warnings and Precautions (5.4)].

Discontinuation Syndrome

Advise patients not to abruptly discontinue ZOLOFT and to discuss any tapering regimen with their healthcare provider. Adverse reactions can occur when ZOLOFT is discontinued [See Warnings and Precautions (5.5)].

Sexual Dysfunction

Advise patients that use of ZOLOFT may cause symptoms of sexual dysfunction in both male and female patients. Inform patients that they should discuss any changes in sexual function and potential management strategies with their healthcare provider [see Warnings and Precautions (5.11)].

Allergic Reactions

Advise patients to notify their healthcare provider if they develop an allergic reaction such as rash, hives, swelling, or difficulty breathing [See Adverse Reactions (6.2)].

Pregnancy

Inform pregnant women that ZOLOFT may cause withdrawal symptoms in the newborn or persistent pulmonary hypertension of the newborn (PPHN) [See Use in Specific Populations (8.1)]. Advise women that there is a pregnancy exposure registry that monitors pregnancy outcomes of women exposed to ZOLOFT during pregnancy.

Distributed by:
Viatris Specialty LLC
Morgantown, WV 26505 U.S.A.

© 2023 Viatris Inc.

ZOLOFT is a registered trademark of Viatris Specialty LLC a Viatris Company.

The brands listed are trademarks of their respective owners.

UPJ:ZLFTTOS:R1

Medication Guide

ZOLOFT (ZOH-loft)

(sertraline hydrochloride)

Tablets and Oral Solution

What is the most important information I should know about ZOLOFT?

ZOLOFT and other antidepressant medicines may cause serious side effects. Call your healthcare provider right away if you have any of the following symptoms, or call 911 if there is an emergency.

1. Suicidal thoughts or actions:
2. ZOLOFT and other antidepressant medicines may increase suicidal thoughts or actions in some people 24 years of age and younger, especially within the first few months of treatment or when the dose is changed.
3. Depression or other serious mental illnesses are the most important causes of suicidal thoughts or actions.
4. Watch for these changes and call your healthcare provider right away if you notice new or sudden changes in mood, behavior, actions, thoughts, or feelings, especially if severe.
  - Pay particular attention to such changes when ZOLOFT is started or when the dose is changed.
  - Keep all follow-up visits with your healthcare provider and call between visits if you are worried about symptoms.

Call your healthcare provider right away if you have any of the following symptoms, or call 911 if an emergency, especially if they are new, worse, or worry you:

  - attempts to commit suicide
  - acting aggressive or violent
  - new or worse depression
  - feeling agitated, restless, angry or irritable
  - an increase in activity or talking more than what is normal for you

- acting on dangerous impulses
- thoughts about suicide or dying
- new or worse anxiety or panic attacks
- trouble sleeping
- other unusual changes in behavior or mood

2. Serotonin Syndrome. This condition can be life-threatening and symptoms may include:

- agitation, hallucinations, coma, or other changes in mental status
- racing heartbeat, high or low blood pressure
- coordination problems or muscle twitching (overactive reflexes)

- nausea, vomiting, or diarrhea
- sweating or fever
- muscle rigidity

3. Increased chance of bleeding: ZOLOFT and other antidepressant medicines may increase your risk of bleeding or bruising, especially if you take the blood thinner warfarin (Coumadin®, Jantoven®), a non-steroidal anti-inflammatory drug (NSAIDs, like ibuprofen or naproxen), or aspirin.
4. Manic episodes. Symptoms may include:

- greatly increased energy
- racing thoughts
- unusually grand ideas

- severe trouble sleeping
- reckless behavior

- excessive happiness or irritability
- talking more or faster than usual

5. Seizures or convulsions.
6. Glaucoma (angle-closure glaucoma). Many antidepressant medicines including ZOLOFT may cause a certain type of eye problem called angle-closure glaucoma. Call your healthcare provider if you have eye pain, changes in your vision, or swelling or redness in or around the eye. Only some people are at risk for these problems. You may want to undergo an eye examination to see if you are at risk and receive preventative treatment if you are.
7. Changes in appetite or weight. Children and adolescents should have height and weight monitored during treatment.
8. Low salt (sodium) levels in the blood. Elderly people may be at greater risk for this. Symptoms may include:

- headache

- weakness or feeling unsteady

- confusion, problems concentrating or thinking, or memory problems

9. Sexual problems (dysfunction). Taking selective serotonin reuptake inhibitors (SSRIs), including ZOLOFT, may cause sexual problems.

Symptoms in males may include:

- Delayed ejaculation or inability to have an ejaculation
- Decreased sex drive
- Problems getting or keeping an erection

Symptoms in females may include:

- Decreased sex drive
- Delayed orgasm or inability to have an orgasm

Talk to your healthcare provider if you develop any changes in your sexual function or if you have any questions or concerns about sexual problems during treatment with ZOLOFT. There may be treatments your healthcare provider can suggest.

Do not stop ZOLOFT without first talking to your healthcare provider. Stopping ZOLOFT too quickly may cause serious symptoms including:

- anxiety, irritability, high or low mood, feeling restless or changes in sleep habits
- headache, sweating, nausea, dizziness
- electric shock-like sensations, shaking, confusion

What is ZOLOFT?

ZOLOFT is a prescription medicine used to treat:

- Major Depressive Disorder (MDD)
- Panic Disorder
- Social Anxiety Disorder

- Obsessive-Compulsive Disorder (OCD)
- Posttraumatic Stress Disorder (PTSD)
- Premenstrual Dysphoric Disorder (PMDD)

It is important to talk with your healthcare provider about the risks of treating depression and also the risks of not treating it. You should discuss all treatment choices with your healthcare provider.

ZOLOFT is safe and effective in treating children with OCD age 6 to 17 years.

It is not known if ZOLOFT is safe and effective for use in children under 6 years of age with OCD or children with other behavior health conditions.

Talk to your healthcare provider if you do not think that your condition is getting better with ZOLOFT treatment.

Who should not take ZOLOFT?

Do not take ZOLOFT if you:

- take a monoamine oxidase inhibitor (MAOI). Ask your healthcare provider or pharmacist if you are not sure if you take an MAOI, including the antibiotic linezolid.
- have taken an MAOI within 2 weeks of stopping ZOLOFT unless directed to do so by your healthcare provider.
- have stopped taking an MAOI in the last 2 weeks unless directed to do so by your healthcare provider.
- take any other medicines that contain sertraline (such as sertraline HCl or sertraline hydrochloride).
- take the antipsychotic medicine pimozide (Orap®) because this can cause serious heart problems.
- are allergic to sertraline or any of the ingredients in ZOLOFT. See the end of this Medication Guide for a complete list of ingredients in ZOLOFT.
- take Antabuse® (disulfiram) (if you are taking the liquid form of ZOLOFT) due to the alcohol content.

People who take ZOLOFT close in time to an MAOI may have serious or even life-threatening side effects. Get medical help right away if you have any of these symptoms:

  - high fever
  - rapid changes in heart rate or blood pressure

- uncontrolled muscle spasms
- confusion

- stiff muscles
- loss of consciousness (pass out)

What should I tell my healthcare provider before taking ZOLOFT?

Before starting ZOLOFT, tell your healthcare provider:

- if you have:

- liver problems
- heart problems
- bipolar disorder or mania

- kidney problems
- or have had seizures or convulsions
- low sodium levels in your blood

- a history of a stroke
- high blood pressure
- or have had bleeding problems

- are pregnant or plan to become pregnant. Your baby may have withdrawal symptoms after birth or may be at increased risk for a serious lung problem at birth. Talk to your healthcare provider about the benefits and risks of taking ZOLOFT during pregnancy.
  - There is a pregnancy registry for females who are exposed to ZOLOFT during pregnancy. The purpose of the registry is to collect information about the health of females exposed to ZOLOFT and their baby. If you or your child become pregnant during treatment with ZOLOFT, talk to your healthcare provider about registering with the National Pregnancy Registry for Antidepressants. You can register by calling 1-866-961-2388 or by visiting online at https://womensmentalhealth.org/research/pregnancyregistry/antidepressants/.
- are breastfeeding or plan to breastfeed. A small amount of ZOLOFT may pass into your breast milk. Talk to your healthcare provider about the best way to feed your baby while taking ZOLOFT.

Tell your healthcare provider about all the medicines that you take, including prescription and over-the-counter medicines, vitamins, and herbal supplements.

Especially tell your healthcare provider if you or your child take:

- medicines used to treat migraine headaches called triptans
- tricyclic antidepressants
- lithium
- tramadol, fentanyl, meperidine, methadone, or other opioids
- tryptophan
- buspirone
- amphetamines
- phenytoin
- St. John’s Wort
- medicines that can affect blood clotting such as aspirin, nonsteroidal anti-inflammatory drugs (NSAIDs), other antiplatelet medicines, warfarin, and other anticoagulants
- diuretics
- medicines used to treat mood, anxiety, psychotic, or thought disorders, including selective serotonin reuptake (SSRIs) and serotonin norepinephrine reuptake inhibitors (SNRIs)

ZOLOFT and some medicines may interact with each other, may not work as well, or may cause serious side effects.

Your healthcare provider or pharmacist can tell you if it is safe to take ZOLOFT with your other medicines. Do not start or stop any medicine while taking ZOLOFT without talking to your healthcare provider first.

How should I take ZOLOFT?

- Take ZOLOFT exactly as prescribed. Your healthcare provider may need to change the dose of ZOLOFT until it is the right dose for you.
- ZOLOFT Tablets may be taken with or without food.
- ZOLOFT Oral Solution may look cloudy or hazy after mixing, this is normal.
- ZOLOFT Oral Solution must be diluted before use:
  - Do not mix ZOLOFT until you are ready to take it.
  - When diluting ZOLOFT Oral Solution, use only water, ginger ale, lemon/lime soda, lemonade, or orange juice.
  - The oral dropper contains latex. If you are sensitive or allergic to latex, ask your healthcare provider or pharmacist about the best way to measure your medicine.
- If you miss a dose of ZOLOFT, take the missed dose as soon as you remember. If it is almost time for the next dose, skip the missed dose and take your next dose at the regular time. Do not take two doses of ZOLOFT at the same time.

If you take too much ZOLOFT, call your healthcare provider or poison control center right away, or go to the nearest hospital emergency room right away.

What should I avoid while taking ZOLOFT?

ZOLOFT can cause sleepiness or may affect your ability to make decisions, think clearly, or react quickly. You should not drive, operate heavy machinery, or do other dangerous activities until you know how ZOLOFT affects you. Do not drink alcohol while you take ZOLOFT.

What are the possible side effects of ZOLOFT?

ZOLOFT may cause serious side effects, including:

- See “What is the most important information I should know about ZOLOFT?”

The most common side effects in adults who take ZOLOFT include:

- nausea, loss of appetite, diarrhea, or indigestion
- increased sweating
- tremor or shaking
- agitation

- change in sleep habits including increased sleepiness or insomnia
- sexual problems including decreased libido and ejaculation failure
- feeling tired or fatigued
- anxiety

The most common side effects in children and adolescents who take ZOLOFT include abnormal increase in muscle movement or agitation, nose bleeds, urinary incontinence, aggressive reaction, possible slowed growth rate, and weight change. Your child’s height and weight should be monitored during treatment with ZOLOFT.

Tell your healthcare provider if you have any side effect that bothers you or that does not go away. These are not all the possible side effects of ZOLOFT. For more information, ask your healthcare provider or pharmacist.

Call your doctor for medical advice about side effects. You may report side effects to the FDA at 1-800-FDA-1088.

How should I store ZOLOFT?

- Store ZOLOFT at room temperature, 68°F to 77°F (20°C to 25°C).
- Keep ZOLOFT bottle closed tightly.

Keep ZOLOFT and all medicines out of the reach of children.

General information about the safe and effective use of ZOLOFT

Medicines are sometimes prescribed for purposes other than those listed in a Medication Guide. Do not use ZOLOFT for a condition for which it was not prescribed. Do not give ZOLOFT to other people, even if they have the same condition. It may harm them.

This Medication Guide summarizes the most important information about ZOLOFT. If you would like more information, talk with your healthcare provider. You may ask your healthcare provider or pharmacist for information about ZOLOFT that is written for healthcare professionals.

For more information about ZOLOFT, call 1-877-446-3679 (1-877-4-INFO-RX).

What are the ingredients in ZOLOFT?

Active ingredient: sertraline hydrochloride

Inactive ingredients:

Tablets: dibasic calcium phosphate dihydrate, D&C Yellow #10 aluminum lake (in 25 mg tablet), FD&C Blue #1 aluminum lake (in 25 mg tablet), FD&C Red #40 aluminum lake (in 25 mg tablet), FD&C Blue #2 aluminum lake (in 50 mg tablet), hydroxypropyl cellulose, hypromellose, magnesium stearate, microcrystalline cellulose, polyethylene glycol, polysorbate 80, sodium starch glycolate, synthetic yellow iron oxide (in 100 mg tablet), and titanium dioxide.

Oral solution: glycerin, alcohol (12%), menthol, butylated hydroxytoluene (BHT)

Distributed by:
Viatris Specialty LLC
Morgantown, WV 26505 U.S.A.

© 2023 Viatris Inc.

ZOLOFT is a registered trademark of Viatris Specialty LLC, a Viatris Company.

The brands listed are trademarks of their respective owners.

UPJ:MG:ZLFTTOS:R1

This Medication Guide has been approved by the U.S. Food and Drug Administration. Revised: 8/2023

PRINCIPAL DISPLAY PANEL – 25 mg

ALWAYS DISPENSE WITH MEDICATION GUIDE

NDC 58151-574-93

Zoloft®
(sertraline hydrochloride)
tablets
25 mg*

30 Tablets Rx only

Store at 20°C to 25°C (68°F to
77°F); excursions permitted
to 15°C to 30°C (59°F to 86°F)
[See USP Controlled Room
Temperature].

DOSAGE AND USE
See accompanying
prescribing information.

*Each tablet contains 28.0 mg
sertraline hydrochloride
equivalent to 25 mg sertraline.

Distributed by:
Viatris Specialty LLC
Morgantown, WV 26505 U.S.A.

© 2023 Viatris Inc.

Made in Germany

RUPJ574H

PRINCIPAL DISPLAY PANEL – 50 mg

ALWAYS DISPENSE WITH MEDICATION GUIDE

NDC 58151-575-93

Zoloft®
(sertraline hydrochloride)
tablets
50 mg*

30 Tablets Rx only

Store at 20°C to 25°C (68°F to
77°F); excursions permitted
to 15°C to 30°C (59°F to 86°F)
[See USP Controlled Room
Temperature].

DOSAGE AND USE
See accompanying
prescribing information.

*Each tablet contains 56.0 mg
sertraline hydrochloride
equivalent to 50 mg sertraline.

Distributed by:
Viatris Specialty LLC
Morgantown, WV 26505 U.S.A.

© 2023 Viatris Inc.

Made in Germany

RUPJ575H

PRINCIPAL DISPLAY PANEL – 100 mg

ALWAYS DISPENSE WITH MEDICATION GUIDE

NDC 58151-576-93

Zoloft®
(sertraline hydrochloride)
tablets
100 mg*

30 Tablets Rx only

Store at 20°C to 25°C (68°F to
77°F); excursions permitted
to 15°C to 30°C (59°F to 86°F)
[See USP Controlled Room
Temperature].

DOSAGE AND USE
See accompanying
prescribing information.

*Each tablet contains 111.9 mg
sertraline hydrochloride
equivalent to 100 mg sertraline.

Distributed by:
Viatris Specialty LLC
Morgantown, WV 26505 U.S.A.

© 2023 Viatris Inc.

Made in Germany

RUPJ576H

PRINCIPAL DISPLAY PANEL – 20 mg/mL

ALWAYS DISPENSE WITH MEDICATION GUIDE

NDC 58151-601-35

Zoloft®
(sertraline hydrochloride)
oral solution
equivalent to
20 mg/mL*
of sertraline

Must Be Diluted
Before Use
(see side panel for instructions)

CALIBRATED DROPPER ENCLOSED

60 mL Rx only

Store at 20°C to 25°C (68°F to
77°F); excursions permitted to
15°C to 30°C (59°F to 86°F)
[See USP Controlled Room
Temperature].

STORE UPRIGHT.

DOSAGE AND USE
See accompanying
prescribing information.

*Each mL of solution contains
22.4 mg sertraline hydrochloride
equivalent to 20 mg of sertraline.

Contains 12% alcohol.

THE PACKAGING OF THIS
PRODUCT CONTAINS
DRY NATURAL RUBBER.

Zoloft Oral Solution Must Be Diluted Before Use.

MIXING INSTRUCTIONS
Just before taking, use the dropper provided to remove the required amount of
ZOLOFT Oral Solution and mix with 4 oz (1/2 cup) of water, ginger ale, lemon/lime
soda, lemonade or orange juice ONLY. Do not mix ZOLOFT Oral Solution with
anything other than the liquids listed. At times, a slight haze may appear after
mixing; this is normal. The medicine should be given immediately after mixing.

DO NOT MIX IN ADVANCE.

Distributed by:
Viatris Specialty LLC
Morgantown, WV 26505 U.S.A.

© 2023 Viatris Inc.

Made in Spain

ZOLOFT is a registered trademark of Viatris Specialty LLC, a Viatris Company.